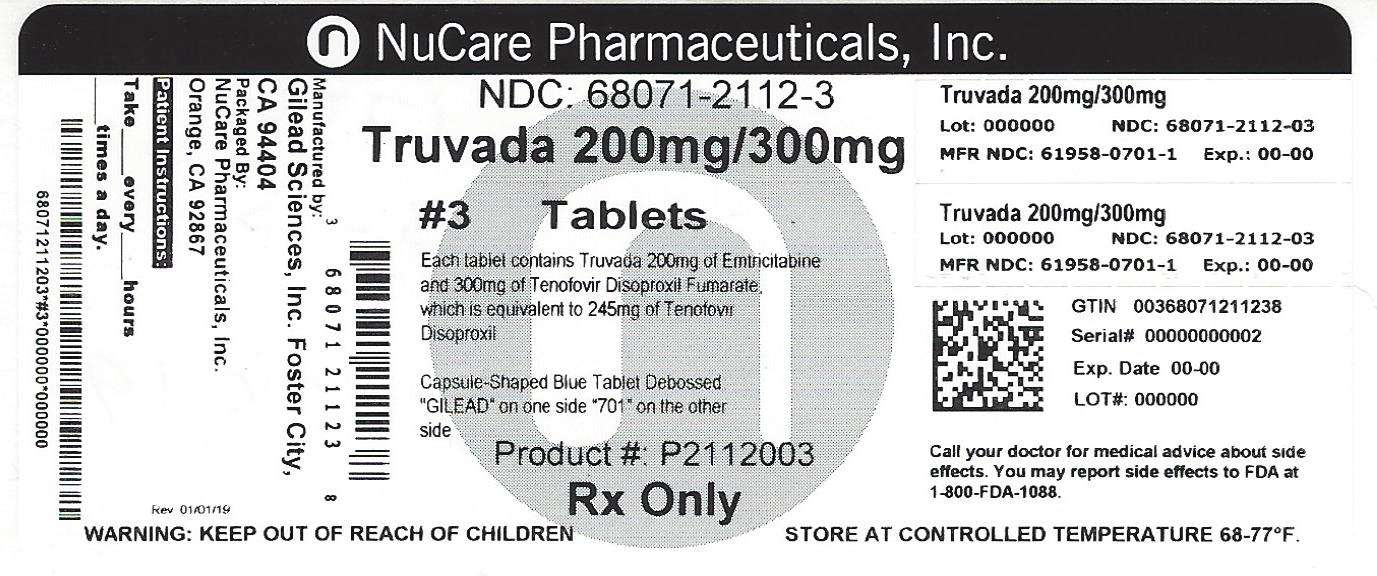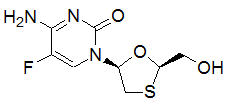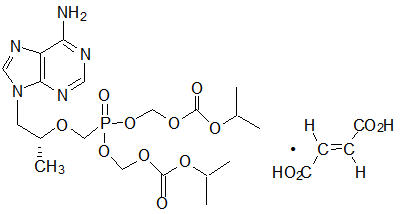 DRUG LABEL: Truvada
NDC: 68071-2112 | Form: TABLET, FILM COATED
Manufacturer: NuCare Pharmaceuticals,Inc.
Category: prescription | Type: HUMAN PRESCRIPTION DRUG LABEL
Date: 20240716

ACTIVE INGREDIENTS: EMTRICITABINE 200 mg/1 1; TENOFOVIR DISOPROXIL FUMARATE 300 mg/1 1
INACTIVE INGREDIENTS: CROSCARMELLOSE SODIUM; LACTOSE MONOHYDRATE; MAGNESIUM STEARATE; CELLULOSE, MICROCRYSTALLINE; STARCH, CORN; WATER; FD&C BLUE NO. 2; ALUMINUM OXIDE; HYPROMELLOSES; TITANIUM DIOXIDE; TRIACETIN

HIGHLIGHTS OF PRESCRIBING INFORMATION

These highlights do not include all the information needed to use TRUVADA safely and effectively. See full prescribing information for TRUVADA.
TRUVADA® (emtricitabine/tenofovir disoproxil fumarate) tablets, for oral use
Initial U.S. Approval: 2004

WARNING: LACTIC ACIDOSIS/SEVERE HEPATOMEGALY WITH STEATOSIS, POST TREATMENT ACUTE EXACERBATION OF HEPATITIS B, and RISK OF DRUG RESISTANCE WITH USE OF TRUVADA FOR PRE-EXPOSURE PROPHYLAXIS (PrEP) IN UNDIAGNOSED EARLY HIV-1 INFECTION

See full prescribing information for complete boxed warning.

- Lactic acidosis and severe hepatomegaly with steatosis, including fatal cases, have been reported with the use of nucleoside analogs, including VIREAD, a component of TRUVADA. (5.1)
- TRUVADA is not approved for the treatment of chronic hepatitis B virus (HBV) infection. Severe acute exacerbations of hepatitis B have been reported in patients coinfected with HIV-1 and HBV who have discontinued TRUVADA. Therefore, hepatic function should be monitored closely in HBV-infected patients who discontinue TRUVADA. If appropriate, initiation of anti-hepatitis B therapy may be warranted. (5.2)
- TRUVADA used for a PrEP indication must only be prescribed to individuals confirmed to be HIV-negative immediately prior to initial use and periodically during use. Drug-resistant HIV-1 variants have been identified with the use of TRUVADA for a PrEP indication following undetected acute HIV-1 infection. Do not initiate TRUVADA for a PrEP indication if signs or symptoms of acute HIV infection are present unless negative infection status is confirmed. (5.9)

RECENT MAJOR CHANGES

Indications and Usage
Treatment of HIV-1 infection (1.1) | 03/2016
Dosage and Administration (2.2) | 03/2016
Warnings and Precautions
Coadministration with Other Products (5.4) | 03/2016

1 INDICATIONS AND USAGE

TRUVADA is a combination of EMTRIVA and VIREAD, both nucleoside analog HIV-1 reverse transcriptase inhibitors.

TRUVADA is indicated in combination with other antiretroviral agents for the treatment of HIV-1 infection in adults and pediatric patients weighing at least 17 kg. (1)

TRUVADA is indicated in combination with safer sex practices for pre-exposure prophylaxis (PrEP) to reduce the risk of sexually acquired HIV-1 in adults at high risk. (1)

2 DOSAGE AND ADMINISTRATION

Treatment of HIV-1 Infection (2.1)

- Recommended dose in adults and pediatric patients weighing greater than or equal to 35 kg: One TRUVADA tablet (containing 200 mg/300 mg of emtricitabine and tenofovir disoproxil fumarate) once daily taken orally with or without food. (2.1)
- Recommended dose in pediatric patients weighing greater than or equal to 17 kg and able to swallow a whole tablet: one TRUVADA low strength tablet (100 mg/150 mg, 133 mg/200 mg, or 167 mg/250 mg based on body weight) once daily taken orally with or without food. (2.2)
- Recommended dose in renally impaired HIV-1 infected adult patients: Creatinine clearance 30–49 mL/min: 1 tablet every 48 hours. (2.4) CrCl below 30 mL/min or hemodialysis: Do not use TRUVADA. (2.4)

Pre-exposure Prophylaxis (2.3)

- Recommended dose in HIV-1 uninfected adults: One tablet (containing 200 mg/300 mg of emtricitabine and tenofovir disoproxil fumarate) once daily taken orally with or without food. (2.3)
- Recommended dose in renally impaired HIV-uninfected individuals: Do not use TRUVADA in HIV-uninfected individuals if CrCl is below 60 mL/min. If a decrease in CrCl is observed in uninfected individuals while using TRUVADA for PrEP, evaluate potential causes and re-assess potential risks and benefits of continued use. (2.4)

3 DOSAGE FORMS AND STRENGTHS

Tablets: 200 mg/300 mg, 167 mg/250 mg, 133 mg/200 mg, and 100 mg/150 mg of emtricitabine and tenofovir disoproxil fumarate, respectively. (3)

4 CONTRAINDICATIONS

Do not use TRUVADA for pre-exposure prophylaxis in individuals with unknown or positive HIV-1 status. TRUVADA should be used in HIV-infected patients only in combination with other antiretroviral agents. (4)

5 WARNINGS AND PRECAUTIONS

- New onset or worsening renal impairment: Can include acute renal failure and Fanconi syndrome. Assess estimated creatinine clearance before initiating treatment with TRUVADA. In patients at risk for renal dysfunction, assess estimated creatinine clearance, serum phosphorus, urine glucose and urine protein before initiating treatment with TRUVADA and periodically during treatment. Avoid administering Truvada with concurrent or recent use of nephrotoxic drugs. (5.3)
- Coadministration with Other Products: Do not use with drugs containing emtricitabine, tenofovir alafenamide or tenofovir disoproxil fumarate including ATRIPLA, COMPLERA, EMTRIVA, GENVOYA, ODEFSEY, STRIBILD, VIREAD; or with drugs containing lamivudine. Do not administer in combination with HEPSERA. (5.4)
- Decreases in bone mineral density (BMD): Consider assessment of BMD in patients with a history of pathologic fracture or other risk factors for osteoporosis or bone loss. (5.5)
- Redistribution/accumulation of body fat: Observed in patients receiving antiretroviral therapy. (5.6)
- Immune reconstitution syndrome: May necessitate further evaluation and treatment. (5.7)
- Triple nucleoside-only regimens: Early virologic failure has been reported in HIV-infected patients. Monitor carefully and consider treatment modification. (5.8)
- Comprehensive management to reduce the risk of acquiring HIV-1: Use as part of a comprehensive prevention strategy including other prevention measures; strictly adhere to dosing schedule. (5.9)
- Management to reduce the risk of acquiring HIV-1 drug resistance:
  Prior to initiating TRUVADA for PrEP - if clinical symptoms consistent with acute viral infection are present and recent (<1 month) exposures are suspected, delay starting PrEP for at least one month and reconfirm negative HIV-1 status or use a test approved by the FDA as an aid in the diagnosis of HIV-1 infection, including acute or primary HIV-1 infection.
  While using TRUVADA for PrEP - HIV-1 screening tests should be repeated at least every 3 months. (5.9)

6 ADVERSE REACTIONS

In HIV-1 infected patients, the most common adverse reactions (incidence greater than or equal to 10%) are diarrhea, nausea, fatigue, headache, dizziness, depression, insomnia, abnormal dreams, and rash. (6.1)

In HIV-1 uninfected individuals in PrEP trials, adverse reactions that were reported by more than 2% of TRUVADA subjects and more frequently than by placebo subjects were headache, abdominal pain and weight decreased. (6.2)

To report SUSPECTED ADVERSE REACTIONS, contact Gilead Sciences, Inc. at 1-800-445-3235 or FDA at 1-800-FDA-1088 or www.fda.gov/medwatch

7 DRUG INTERACTIONS

- Didanosine: Tenofovir disoproxil fumarate increases didanosine concentrations. Use with caution and monitor for evidence of didanosine toxicity (e.g., pancreatitis, neuropathy) when coadministered. Consider dose reductions or discontinuations of didanosine if warranted. (7.1)
- HIV-1 protease inhibitors: Coadministration decreases atazanavir concentrations and increases tenofovir concentrations. When coadministered with TRUVADA, use atazanavir given with ritonavir. Coadministration of TRUVADA with atazanavir and ritonavir, darunavir and ritonavir, or lopinavir/ritonavir increases tenofovir concentrations. Monitor for evidence of tenofovir toxicity. (7.2)

8 USE IN SPECIFIC POPULATIONS

- Nursing mothers: Women infected with HIV-1 should be instructed not to breast feed. (8.3)

FULL PRESCRIBING INFORMATION

WARNING: LACTIC ACIDOSIS/SEVERE HEPATOMEGALY WITH STEATOSIS, POST TREATMENT ACUTE EXACERBATION OF HEPATITIS B, and RISK OF DRUG RESISTANCE WITH USE OF TRUVADA FOR PRE-EXPOSURE PROPHYLAXIS (PrEP) IN UNDIAGNOSED EARLY HIV-1 INFECTION

Lactic acidosis and severe hepatomegaly with steatosis, including fatal cases, have been reported with the use of nucleoside analogs, including VIREAD, a component of TRUVADA, in combination with other antiretrovirals [see Warnings and Precautions (5.1)] .

TRUVADA is not approved for the treatment of chronic hepatitis B virus (HBV) infection and the safety and efficacy of TRUVADA have not been established in patients coinfected with HBV and HIV-1. Severe acute exacerbations of hepatitis B have been reported in patients who are coinfected with HBV and HIV-1 and have discontinued TRUVADA. Therefore, hepatic function should be monitored closely with both clinical and laboratory follow-up for at least several months in patients who are infected with HBV and discontinue TRUVADA. If appropriate, initiation of anti-hepatitis B therapy may be warranted [see Warnings and Precautions (5.2)] .

TRUVADA used for a PrEP indication must only be prescribed to individuals confirmed to be HIV-negative immediately prior to initiating and periodically (at least every 3 months) during use. Drug-resistant HIV-1 variants have been identified with use of TRUVADA for a PrEP indication following undetected acute HIV-1 infection. Do not initiate TRUVADA for a PrEP indication if signs or symptoms of acute HIV-1 infection are present unless negative infection status is confirmed [see Warnings and Precautions (5.9)] .

1 INDICATIONS AND USAGE

1.1 Treatment of HIV-1 Infection

TRUVADA®, a combination of EMTRIVA® and VIREAD®, is indicated in combination with other antiretroviral agents for the treatment of HIV-1 infection in adults and pediatric patients weighing at least 17 kg [see Dosage and Administration (2) and Clinical Studies (14)] .

The following points should be considered when initiating therapy with TRUVADA for the treatment of HIV-1 infection:The following points should be considered when initiating therapy with TRUVADA for the treatment of HIV-1 infection:

- It is not recommended that TRUVADA be used as a component of a triple nucleoside regimen.
- TRUVADA should not be coadministered with ATRIPLA®, COMPLERA®, EMTRIVA, GENVOYA®, ODEFSEY®, STRIBILD®, VIREAD or lamivudine-containing products [see Warnings and Precautions (5.4)] .
- In treatment experienced patients, the use of TRUVADA should be guided by laboratory testing and treatment history [see Microbiology (12.4)] .

1.2 Pre-Exposure Prophylaxis

TRUVADA is indicated in combination with safer sex practices for pre-exposure prophylaxis (PrEP) to reduce the risk of sexually acquired HIV-1 in adults at high risk. This indication is based on clinical trials in men who have sex with men (MSM) at high risk for HIV-1 infection and in heterosexual serodiscordant couples [see Clinical Studies (14.2, 14.3)] .

When considering TRUVADA for pre-exposure prophylaxis the following factors may help to identify individuals at high risk:

- has partner(s) known to be HIV-1 infected, or
- engages in sexual activity within a high prevalence area or social network and one or more of the following:
  - inconsistent or no condom use
  - diagnosis of sexually transmitted infections
  - exchange of sex for commodities (such as money, food, shelter, or drugs)
  - use of illicit drugs or alcohol dependence
  - incarceration
  - partner(s) of unknown HIV-1 status with any of the factors listed above

When prescribing TRUVADA for pre-exposure prophylaxis, healthcare providers must:

- prescribe TRUVADA as part of a comprehensive prevention strategy because TRUVADA is not always effective in preventing the acquisition of HIV-1 infection [see Warnings and Precautions (5.9)] ;
- counsel all uninfected individuals to strictly adhere to the recommended TRUVADA dosing schedule because the effectiveness of TRUVADA in reducing the risk of acquiring HIV-1 was strongly correlated with adherence as demonstrated by measurable drug levels in clinical trials [see Warnings and Precautions (5.9)] ;
- confirm a negative HIV-1 test immediately prior to initiating TRUVADA for a PrEP indication. If clinical symptoms consistent with acute viral infection are present and recent (<1 month) exposures are suspected, delay starting PrEP for at least one month and reconfirm HIV-1 status or use a test approved by the FDA as an aid in the diagnosis of HIV-1 infection, including acute or primary HIV-1 infection [see Warnings and Precautions (5.9)] ; and
- screen for HIV-1 infection at least once every 3 months while taking TRUVADA for PrEP.

2 DOSAGE AND ADMINISTRATION

2.1 Recommended Dose for Treatment of HIV-1 Infection in Adults and Pediatric Patients Weighing 35 Kg or More

The recommended dose of TRUVADA in adults and in pediatric patients with body weight greater than or equal to 35 kg is one tablet (containing 200 mg of emtricitabine and 300 mg of tenofovir disoproxil fumarate) once daily taken orally with or without food.

2.2 Recommended Dose for Treatment of HIV-1 Infection in Pediatric Patients Weighing at Least 17 kg and Able to Swallow a Whole Tablet

The recommended oral dose for pediatric patients weighing greater than or equal to 17 kg and who are able to swallow a whole tablet, is one TRUVADA low strength tablet (emtricitabine [FTC]/tenofovir disoproxil fumarate [TDF]) (167 mg/250 mg, 133 mg/200 mg, or 100 mg/150 mg based on body weight) taken orally once daily with or without food.

The recommended oral dosage of TRUVADA low strength tablets is presented in Table 1. Weight should be monitored periodically and the TRUVADA dose adjusted accordingly.

Table 1 Dosing for Pediatric Patients Weighing 17 kg to less than 35 kg using TRUVADA Low Strength Tablets
Body Weight (kg) | Dosing of FTC (mg)/TDF (mg)
17 to less than 22 | one 100/150 tablet once daily
22 to less than 28 | one 133/200 tablet once daily
28 to less than 35 | one 167/250 tablet once daily

2.3 Recommended Dose for Pre-exposure Prophylaxis

The dose of TRUVADA in HIV-1 uninfected adults is one tablet (containing 200 mg of emtricitabine and 300 mg of tenofovir disoproxil fumarate) once daily taken orally with or without food.

2.4 Dose Adjustment for Renal Impairment

Treatment of HIV-1 Infection

Significantly increased drug exposures occurred when EMTRIVA or VIREAD were administered to subjects with moderate to severe renal impairment [see EMTRIVA or VIREAD Package Insert]. Therefore, adjust the dosing interval of TRUVADA in HIV-1 infected adult patients with baseline creatinine clearance 30–49 mL/min using the recommendations in Table 2. These dosing interval recommendations are based on modeling of single-dose pharmacokinetic data in non-HIV infected subjects. The safety and effectiveness of these dosing interval adjustment recommendations have not been clinically evaluated in patients with moderate renal impairment, therefore clinical response to treatment and renal function should be closely monitored in these patients [see Warnings and Precautions (5.3)] .

No dose adjustment is necessary for HIV-1 infected patients with mild renal impairment (creatinine clearance 50–80 mL/min). No data are available to make dose recommendations in pediatric patients with renal impairment.

Table 2 Dosage Adjustment for HIV-1 Infected Adult Patients with Altered Creatinine Clearance
 | Creatinine Clearance (mL/min) [Calculated using ideal (lean) body weight]
 | ≥50 | 30–49 | <30 (Including Patients Requiring Hemodialysis)
Recommended Dosing Interval | Every 24 hours | Every 48 hours | TRUVADA should not be administered.

Routine monitoring of estimated creatinine clearance, serum phosphorus, urine glucose, and urine protein should be performed in all individuals with mild renal impairment [see Warnings and Precautions (5.3)] .

Pre-exposure Prophylaxis

Do not use TRUVADA for a PrEP indication in HIV-1 uninfected individuals with estimated creatinine clearance below 60 mL/min [see Warnings and Precautions (5.3)] .

Routine monitoring of estimated creatinine clearance, serum phosphorus, urine glucose, and urine protein should be performed in all individuals with mild renal impairment. If a decrease in estimated creatinine clearance is observed in uninfected individuals while using TRUVADA for PrEP, evaluate potential causes and re-assess potential risks and benefits of continued use [see Warnings and Precautions (5.3)] .

3 DOSAGE FORMS AND STRENGTHS

TRUVADA tablets are available in four dose strengths:

- Tablet: 100 mg of emtricitabine and 150 mg of tenofovir disoproxil fumarate (equivalent to 123 mg of tenofovir disoproxil): blue, oval-shaped, film-coated, debossed with "GSI" on one side and with "703" on the other side.
- Tablet: 133 mg of emtricitabine and 200 mg of tenofovir disoproxil fumarate (equivalent to 163 mg of tenofovir disoproxil): blue, rectangular-shaped, film-coated, debossed with "GSI" on one side and with "704" on the other side.
- Tablet: 167 mg of emtricitabine and 250 mg of tenofovir disoproxil fumarate (equivalent to 204 mg of tenofovir disoproxil): blue, modified capsule-shaped, film-coated, debossed with "GSI" on one side and with "705" on the other side.
- Tablet: 200 mg of emtricitabine and 300 mg of tenofovir disoproxil fumarate (equivalent to 245 mg of tenofovir disoproxil): blue, capsule-shaped, film-coated, debossed with "GILEAD" on one side and with "701" on the other side.

4 CONTRAINDICATIONS

Do not use TRUVADA for pre-exposure prophylaxis in individuals with unknown or positive HIV-1 status. TRUVADA should be used in HIV-infected patients only in combination with other antiretroviral agents.

5 WARNINGS AND PRECAUTIONS

5.1 Lactic Acidosis/Severe Hepatomegaly with Steatosis

Lactic acidosis and severe hepatomegaly with steatosis, including fatal cases, have been reported with the use of nucleoside analogs, including VIREAD, a component of TRUVADA, in combination with other antiretrovirals. A majority of these cases have been in women. Obesity and prolonged nucleoside exposure may be risk factors. Particular caution should be exercised when administering nucleoside analogs to any patient or uninfected individual with known risk factors for liver disease; however, cases have also been reported in HIV-1 infected patients with no known risk factors. Treatment with TRUVADA should be suspended in any patient or uninfected individual who develops clinical or laboratory findings suggestive of lactic acidosis or pronounced hepatotoxicity (which may include hepatomegaly and steatosis even in the absence of marked transaminase elevations).

5.2 HBV Infection

It is recommended that all individuals be tested for the presence of chronic hepatitis B virus (HBV) before initiating TRUVADA. TRUVADA is not approved for the treatment of chronic HBV infection and the safety and efficacy of TRUVADA have not been established in patients infected with HBV. Severe acute exacerbations of hepatitis B have been reported in patients who are coinfected with HBV and HIV-1 and have discontinued TRUVADA. In some patients infected with HBV and treated with EMTRIVA, the exacerbations of hepatitis B were associated with liver decompensation and liver failure. Patients who are infected with HBV should be closely monitored with both clinical and laboratory follow-up for at least several months after stopping treatment with TRUVADA. If appropriate, initiation of anti-hepatitis B therapy may be warranted. HBV-uninfected individuals should be offered vaccination.

5.3 New Onset or Worsening Renal Impairment

Emtricitabine and tenofovir are principally eliminated by the kidney. Renal impairment, including cases of acute renal failure and Fanconi syndrome (renal tubular injury with severe hypophosphatemia), has been reported with the use of VIREAD [see Adverse Reactions (6.3)] .

It is recommended that estimated creatinine clearance be assessed in all individuals prior to initiating therapy and as clinically appropriate during therapy with TRUVADA. In patients at risk of renal dysfunction, including patients who have previously experienced renal events while receiving HEPSERA®, it is recommended that estimated creatinine clearance, serum phosphorus, urine glucose, and urine protein be assessed prior to initiation of TRUVADA, and periodically during TRUVADA therapy.

TRUVADA should be avoided with concurrent or recent use of a nephrotoxic agent (e.g., high-dose or multiple non-steroidal anti-inflammatory drugs (NSAIDs)) [see Drug Interactions (7.4)] . Cases of acute renal failure after initiation of high dose or multiple NSAIDs have been reported in HIV-infected patients with risk factors for renal dysfunction who appeared stable on tenofovir disoproxil fumarate (tenofovir DF). Some patients required hospitalization and renal replacement therapy. Alternatives to NSAIDs should be considered, if needed, in patients at risk for renal dysfunction.

Persistent or worsening bone pain, pain in extremities, fractures and/or muscular pain or weakness may be manifestations of proximal renal tubulopathy and should prompt an evaluation of renal function in at-risk patients.

Treatment of HIV-1 Infection

Dosing interval adjustment of TRUVADA and close monitoring of renal function are recommended in all patients with estimated creatinine clearance 30–49 mL/min [see Dosage and Administration (2.4)] . No safety or efficacy data are available in patients with renal impairment who received TRUVADA using these dosing guidelines, so the potential benefit of TRUVADA therapy should be assessed against the potential risk of renal toxicity. TRUVADA should not be administered to patients with estimated creatinine clearance below 30 mL/min or patients requiring hemodialysis.

Pre-exposure Prophylaxis

TRUVADA for a PrEP indication should not be used if estimated creatinine clearance is less than 60 mL/min. If a decrease in estimated creatinine clearance is observed in uninfected individuals while using TRUVADA for PrEP, evaluate potential causes and re-assess potential risks and benefits of continued use [see Dosage and Administration (2.4)] .

5.4 Coadministration with Other Products

TRUVADA is a fixed-dose combination of emtricitabine and tenofovir disoproxil fumarate. Do not coadminister TRUVADA with other drugs containing emtricitabine or tenofovir disoproxil fumarate, or containing tenofovir alafenamide, including ATRIPLA, COMPLERA, EMTRIVA, GENVOYA, ODEFSEY, STRIBILD, or VIREAD. Due to similarities between emtricitabine and lamivudine, do not coadminister TRUVADA with other drugs containing lamivudine, including Combivir (lamivudine/zidovudine), Dutrebis (lamivudine/raltegravir) , Epivir or Epivir-HBV (lamivudine), Epzicom (abacavir sulfate/lamivudine), Triumeq (abacavir sulfate/dolutegravir/lamivudine), or Trizivir (abacavir sulfate/lamivudine/zidovudine).

Do not coadminister TRUVADA with HEPSERA (adefovir dipivoxil) Do not coadminister TRUVADA with HEPSERA (adefovir dipivoxil) .

5.5 Bone Effects of Tenofovir DF

Bone Mineral Density:

In clinical trials in HIV-1 infected adults and in a clinical trial of HIV-1 uninfected individuals, tenofovir DF was associated with slightly greater decreases in bone mineral density (BMD) and increases in biochemical markers of bone metabolism, suggesting increased bone turnover relative to comparators [see Adverse Reactions (6.2) and VIREAD prescribing information ]. Serum parathyroid hormone levels and 1,25 Vitamin D levels were also higher in subjects receiving tenofovir DF.

Clinical trials evaluating tenofovir DF in pediatric and adolescent subjects were conducted. Under normal circumstances, BMD increases rapidly in pediatric patients. In HIV-1 infected subjects aged 2 years to less than 18 years, bone effects were similar to those observed in adult subjects and suggest increased bone turnover. Total body BMD gain was less in the tenofovir DF treated HIV-1 infected pediatric subjects as compared to the control groups. Similar trends were observed in chronic hepatitis B infected adolescent subjects aged 12 years to less than 18 years. In all pediatric trials, skeletal growth (height) appeared to be unaffected. For more information, consult the VIREAD prescribing information.

The effects of tenofovir DF-associated changes in BMD and biochemical markers on long-term bone health and future fracture risk are unknown. Assessment of BMD should be considered for adult and pediatric patients who have a history of pathologic bone fracture or other risk factors for osteoporosis or bone loss. Although the effect of supplementation with calcium and vitamin D was not studied, such supplementation may be beneficial. If bone abnormalities are suspected then appropriate consultation should be obtained.

Mineralization Defects:

Cases of osteomalacia associated with proximal renal tubulopathy, manifested as bone pain or pain in extremities and which may contribute to fractures, have been reported in association with the use of tenofovir DF [see Adverse Reactions (6.3)] . Arthralgias and muscle pain or weakness have also been reported in cases of proximal renal tubulopathy. Hypophosphatemia and osteomalacia secondary to proximal renal tubulopathy should be considered in patients at risk of renal dysfunction who present with persistent or worsening bone or muscle symptoms while receiving products containing tenofovir DF [see Warnings and Precautions (5.3)].

5.6 Fat Redistribution

Redistribution/accumulation of body fat including central obesity, dorsocervical fat enlargement (buffalo hump), peripheral wasting, facial wasting, breast enlargement, and "cushingoid appearance" have been observed in HIV-1 infected patients receiving antiretroviral therapy. The mechanism and long-term consequences of these events are currently unknown. A causal relationship has not been established.

5.7 Immune Reconstitution Syndrome

Immune reconstitution syndrome has been reported in HIV-1 infected patients treated with combination antiretroviral therapy, including TRUVADA. During the initial phase of combination antiretroviral treatment, HIV-1 infected patients whose immune system responds may develop an inflammatory response to indolent or residual opportunistic infections [such as Mycobacterium avium infection, cytomegalovirus, Pneumocystis jirovecii pneumonia (PCP), or tuberculosis], which may necessitate further evaluation and treatment.

Autoimmune disorders (such as Graves' disease, polymyositis, and Guillain-Barré syndrome) have also been reported to occur in the setting of immune reconstitution, however, the time to onset is more variable, and can occur many months after initiation of treatment.

5.8 Early Virologic Failure

Clinical trials in HIV-1 infected subjects have demonstrated that certain regimens that only contain three nucleoside reverse transcriptase inhibitors (NRTI) are generally less effective than triple drug regimens containing two NRTIs in combination with either a non-nucleoside reverse transcriptase inhibitor or a HIV-1 protease inhibitor. In particular, early virologic failure and high rates of resistance substitutions have been reported. Triple nucleoside regimens should therefore be used with caution. Patients on a therapy utilizing a triple nucleoside-only regimen should be carefully monitored and considered for treatment modification.

5.9 Comprehensive Management to Reduce the Risk of Acquiring HIV-1

Use TRUVADA for pre-exposure prophylaxis only as part of a comprehensive prevention strategy that includes other prevention measures, such as safer sex practices, because TRUVADA is not always effective in preventing the acquisition of HIV-1 [see Clinical Studies (14.2 and 14.3)] .

- Counsel uninfected individuals about safer sex practices that include consistent and correct use of condoms, knowledge of their HIV-1 status and that of their partner(s), and regular testing for other sexually transmitted infections that can facilitate HIV-1 transmission (such as syphilis and gonorrhea).
- Inform uninfected individuals about and support their efforts in reducing sexual risk behavior.

Use TRUVADA to reduce the risk of acquiring HIV-1 only in individuals confirmed to be HIV-negative. HIV-1 resistance substitutions may emerge in individuals with undetected HIV-1 infection who are taking only TRUVADA, because TRUVADA alone does not constitute a complete treatment regimen for HIV-1 treatment [see Microbiology (12.4)] ; therefore, care should be taken to minimize drug exposure in HIV-infected individuals.

- Many HIV-1 tests, such as rapid tests, detect anti-HIV antibodies and may not identify HIV-1 during the acute stage of infection. Prior to initiating TRUVADA for a PrEP indication, evaluate seronegative individuals for current or recent signs or symptoms consistent with acute viral infections (e.g., fever, fatigue, myalgia, skin rash, etc.) and ask about potential exposure events (e.g., unprotected, or condom broke during sex with an HIV-1 infected partner) that may have occurred within the last month.
  - If clinical symptoms consistent with acute viral infection are present and recent (<1 month) exposures are suspected, delay starting PrEP for at least one month and reconfirm HIV-1 status or use a test approved by the FDA as an aid in the diagnosis of HIV-1 infection, including acute or primary HIV-1 infection.
- While using TRUVADA for a PrEP indication, HIV-1 screening tests should be repeated at least every 3 months. If symptoms consistent with acute HIV-1 infection develop following a potential exposure event, PrEP should be discontinued until negative infection status is confirmed using a test approved by the FDA as an aid in the diagnosis of HIV-1, including acute or primary HIV-1 infection.

Counsel uninfected individuals to strictly adhere to the recommended TRUVADA dosing schedule. The effectiveness of TRUVADA in reducing the risk of acquiring HIV-1 is strongly correlated with adherence as demonstrated by measurable drug levels in clinical trials [see Clinical Studies (14.2 and 14.3)] .

6 ADVERSE REACTIONS

The following adverse reactions are discussed in other sections of the labeling:

- Lactic Acidosis/Severe Hepatomegaly with Steatosis [see Boxed Warning, Warnings and Precautions (5.1)] .
- Severe Acute Exacerbations of hepatitis B [see Boxed Warning, Warnings and Precautions (5.2)] .
- New Onset or Worsening Renal Impairment [see Warnings and Precautions (5.3)] .
- Bone Effects of Tenofovir DF [see Warnings and Precautions (5.5)] .
- Immune Reconstitution Syndrome [see Warnings and Precautions (5.7)] .

6.1 Adverse Reactions from Clinical Trials Experience in HIV-1 Infected Subjects

Because clinical trials are conducted under widely varying conditions, adverse reaction rates observed in the clinical trials of a drug cannot be directly compared to rates in the clinical trials of another drug and may not reflect the rates observed in practice.

Clinical Trials in Adult Subjects

The most common adverse reactions (incidence greater than or equal to 10%, any severity) occurring in Study 934, an active-controlled clinical trial of efavirenz, emtricitabine, and tenofovir disoproxil fumarate, include diarrhea, nausea, fatigue, headache, dizziness, depression, insomnia, abnormal dreams, and rash. See also Table 3 for the frequency of treatment-emergent adverse reactions (Grades 2–4) occurring in greater than or equal to 5% of subjects treated in any treatment group in this trial.

Skin discoloration, manifested by hyperpigmentation on the palms and/or soles, was generally mild and asymptomatic. The mechanism and clinical significance are unknown.

Study 934 - Treatment Emergent Adverse Reactions: In Study 934, 511 antiretroviral-naïve subjects received either VIREAD + EMTRIVA administered in combination with efavirenz (N=257) or zidovudine/lamivudine administered in combination with efavirenz (N=254) for 144 weeks. Subjects had a mean age of 40 years (range 20 to 73 years) and were predominantly male (88%). Overall, 65% were White, 17% were Black, and 13% were Hispanic. Adverse reactions observed in this trial were generally consistent with those seen in other trials in treatment-experienced or treatment-naïve subjects receiving VIREAD and/or EMTRIVA (Table 3).

Table 3 Selected Treatment-Emergent Adverse Reactions [Frequencies of adverse reactions are based on all treatment-emergent adverse events, regardless of relationship to study drug.] (Grades 2–4) Reported in ≥5% in Any Treatment Group in Study 934 (0–144 Weeks)
 | FTC+TDF+EFV [From Weeks 96 to 144 of the trial, subjects received TRUVADA with efavirenz in place of VIREAD + EMTRIVA with efavirenz.] | AZT/3TC+EFV
 | N=257 | N=254
Gastrointestinal Disorder
Diarrhea | 9% | 5%
Nausea | 9% | 7%
Vomiting | 2% | 5%
General Disorders and Administration Site Condition
Fatigue | 9% | 8%
Infections and Infestations
Sinusitis | 8% | 4%
Upper respiratory tract infections | 8% | 5%
Nasopharyngitis | 5% | 3%
Nervous System Disorders
Headache | 6% | 5%
Dizziness | 8% | 7%
Psychiatric Disorders
Depression | 9% | 7%
Insomnia | 5% | 7%
Skin and Subcutaneous Tissue Disorders
Rash event [Rash event includes rash, exfoliative rash, rash generalized, rash macular, rash maculo-papular, rash pruritic, and rash vesicular.] | 7% | 9%

Laboratory Abnormalities: Laboratory abnormalities observed in this trial were generally consistent with those seen in other trials of VIREAD and/or EMTRIVA (Table 4).

Table 4 Significant Laboratory Abnormalities Reported in ≥1% of Subjects in Any Treatment Group in Study 934 (0–144 Weeks)
 | FTC+TDF+EFV [From Weeks 96 to 144 of the trial, subjects received TRUVADA with efavirenz in place of VIREAD + EMTRIVA with efavirenz.] | AZT/3TC+EFV
 | N=257 | N=254
Any ≥ Grade 3 Laboratory Abnormality | 30% | 26%
Fasting Cholesterol (>240 mg/dL) | 22% | 24%
Creatine Kinase (M: >990 U/L) (F: >845 U/L) | 9% | 7%
Serum Amylase (>175 U/L) | 8% | 4%
Alkaline Phosphatase (>550 U/L) | 1% | 0%
AST (M: >180 U/L) (F: >170 U/L) | 3% | 3%
ALT (M: >215 U/L) (F: >170 U/L) | 2% | 3%
Hemoglobin (<8.0 mg/dL) | 0% | 4%
Hyperglycemia (>250 mg/dL) | 2% | 1%
Hematuria (>75 RBC/HPF) | 3% | 2%
Glycosuria (≥3+) | <1% | 1%
Neutrophils (<750/mm^3) | 3% | 5%
Fasting Triglycerides (>750 mg/dL) | 4% | 2%

In addition to the events described above for Study 934, other adverse reactions that occurred in at least 5% of subjects receiving EMTRIVA or VIREAD with other antiretroviral agents in clinical trials include anxiety, arthralgia, increased cough, dyspepsia, fever, myalgia, pain, abdominal pain, back pain, paresthesia, peripheral neuropathy (including peripheral neuritis and neuropathy), pneumonia, and rhinitis.

In addition to the laboratory abnormalities described above for Study 934, Grades 3–4 laboratory abnormalities of increased bilirubin (>2.5 × ULN), increased pancreatic amylase (>2.0 × ULN), increased or decreased serum glucose (<40 or >250 mg/dL), and increased serum lipase (>2.0 × ULN) occurred in up to 3% of subjects treated with EMTRIVA or VIREAD with other antiretroviral agents in clinical trials.

Clinical Trials in Pediatric Subjects

Emtricitabine: In addition to the adverse reactions reported in adults, anemia and hyperpigmentation were observed in 7% and 32%, respectively, of pediatric subjects (3 months to less than 18 years of age) who received treatment with EMTRIVA in the larger of two open-label, uncontrolled pediatric trials (N=116). For additional information, consult the EMTRIVA prescribing information.

Tenofovir Disoproxil Fumarate: In pediatric clinical trials (Studies 352 and 321) conducted in 184 HIV-1 infected subjects 2 to less than 18 years of age, the adverse reactions observed in pediatric subjects who received treatment with VIREAD were consistent with those observed in clinical trials of VIREAD in adults.

Eighty-nine pediatric subjects (2 to less than 12 years of age) received VIREAD in Study 352 for a median exposure of 104 weeks. Of these, 4 subjects discontinued from the trial due to adverse reactions consistent with proximal renal tubulopathy. Three of these 4 subjects presented with hypophosphatemia and also had decreases in total body or spine BMD Z score [see Warnings and Precautions (5.5)]. For additional information, consult the VIREAD prescribing information.

6.2 Adverse Reactions from Clinical Trial Experience in HIV-1 Uninfected Adult Subjects

No new adverse reactions to TRUVADA were identified from two randomized placebo-controlled clinical trials (iPrEx, Partners PrEP), in which 2,830 HIV-1 uninfected adults received TRUVADA once daily for pre-exposure prophylaxis. Subjects were followed for a median of 71 weeks and 87 weeks, respectively. These trials enrolled HIV-negative individuals ranging in age from 18 to 67 years. The iPrEx trial enrolled only men or transgender women of Hispanic/Latino (72%), White (18%), Black (9%) and Asian (5%) race. The Partners PrEP trial enrolled both men (61–64% across treatment groups) and women in Kenya and Uganda. Table 5 provides a list of all adverse events that occurred in 2% or more of subjects in any treatment group in the iPrEx and Partners PrEP trials.

Laboratory Abnormalities: Table 6 provides a list of laboratory abnormalities observed in both trials. Six subjects in the TDF-containing arms of the Partners PrEP trial discontinued participation in the study due to an increase in blood creatinine compared with no discontinuations in the placebo group. One subject in the TRUVADA arm of the iPrEx trial discontinued from the study due to an increase in blood creatinine and another due to low phosphorous.

In addition to the laboratory abnormalities described above, Grade 1 proteinuria (1+) occurred in 6% of subjects receiving TRUVADA in the iPrEx trial. Grades 2–3 proteinuria (2–4+) and glycosuria (3+) occurred in less than 1% of subjects treated with TRUVADA in the iPrEx trial and Partners PrEP trial.

Table 5 Selected Adverse Events (All Grades) Reported in ≥2% in Any Treatment Group in the iPrEx Trial and Partners PrEP Trial
 | iPrEx Trial |  | Partners PrEP Trial
 | FTC/TDF (N=1251) | Placebo (N=1248) | FTC/TDF (N=1579) | Placebo (N=1584)
Gastrointestinal Disorders
Diarrhea | 7% | 8% | 2% | 3%
Abdominal pain | 4% | 2% | - [Not reported or reported below 2%.] | -
Infections and Infestations
Pharyngitis | 13% | 16% | - | -
Urethritis | 5% | 7% | - | -
Urinary tract infection | 2% | 2% | 5% | 7%
Syphilis | 6% | 5% | - | -
Secondary syphilis | 6% | 4% | - | -
Anogenital warts | 2% | 3% | - | -
Musculoskeletal and Connective Tissue Disorders
Back pain | 5% | 5% | - | -
Nervous System Disorders
Headache | 7% | 6% | - | -
Psychiatric Disorders
Depression | 6% | 7% | - | -
Anxiety | 3% | 3% | - | -
Reproductive System and Breast Disorders
Genital ulceration | 2% | 2% | 2% | 2%
Investigations
Weight decreased | 3% | 2% | - | -

Table 6 Laboratory Abnormalities (Highest Toxicity Grade) Reported for Each Subject in the iPrEx Trial and Partners PrEP Trial
 |  |  | iPrEx Trial |  | Partners PrEP Trial
 | Grade [Grading is per DAIDS criteria.] |  | FTC/TDF (N= 1251) | Placebo (N= 1248) | FTC/TDF (N=1579) | Placebo (N=1584)
Creatinine | 1 | (1.1–1.3 × ULN) | 27 (2%) | 21 (2%) | 18 (1%) | 12 (<1%)
 | 2–4 | (> 1.4 × ULN) | 5 (<1%) | 3 (<1%) | 2 (<1%) | 1 (<1%)
Phosphorus | 1 | (2.5 – <LLN mg/dL) | 81 (7%) | 110 (9%) | NR [Grade 1 phosphorus was not reported for the Partners PrEP trial.] | NR
Phosphorus | 2–4 | (<2.0 mg/dL) | 123 (10%) | 101 (8%) | 140 (9%) | 136 (9%)
AST | 1 | (1.25–<2.5 × ULN) | 175 (14%) | 175 (14%) | 20 (1%) | 25 (2%)
AST | 2–4 | (> 2.6 × ULN) | 57 (5%) | 61 (5%) | 10 (<1%) | 4 (<1%)
ALT | 1 | (1.25–<2.5 × ULN) | 178 (14%) | 194 (16%) | 21 (1%) | 13 (<1%)
ALT | 2–4 | (> 2.6 × ULN) | 84 (7%) | 82 (7%) | 4 (<1%) | 6 (<1%)
Hemoglobin | 1 | (8.5 – 10 mg/dL) | 49 (4%) | 62 (5%) | 56 (4%) | 39 (2%)
Hemoglobin | 2–4 | (<9.4 mg/dL) | 13 (1%) | 19 (2%) | 28 (2%) | 39 (2%)
Neutrophils | 1 | (1000–1300/mm^3) | 23 (2%) | 25 (2%) | 208 (13%) | 163 (10%)
Neutrophils | 2–4 | (<750/mm^3) | 7 (<1%) | 7 (<1%) | 73 (5%) | 56 (3%)

Changes in Bone Mineral Density:

In clinical trials of HIV-1 uninfected individuals, decreases in BMD were observed. In the iPrEx trial, a substudy of 503 subjects found mean changes from baseline in BMD ranging from –0.4% to –1.0% across total hip, spine, femoral neck, and trochanter in the TRUVADA group compared with the placebo group, which returned toward baseline after discontinuation of treatment. Thirteen percent of subjects receiving TRUVADA versus 6% of subjects receiving placebo lost at least 5% of BMD at the spine during treatment. Bone fractures were reported in 1.7% of the TRUVADA group compared with 1.4% in the placebo group. No correlation between BMD and fractures was noted [see Clinical Studies (14.2)] . The Partners PrEP trial found similar fracture rates between treatment and placebo groups (0.8% and 0.6%, respectively). No BMD evaluations were performed during this trial [see Clinical Studies (14.3)] .

6.3 Postmarketing Experience

The following adverse reactions have been identified during postapproval use of VIREAD. No additional adverse reactions have been identified during postapproval use of EMTRIVA. Because postmarketing reactions are reported voluntarily from a population of uncertain size, it is not always possible to reliably estimate their frequency or establish a causal relationship to drug exposure.

Immune System Disorders
allergic reaction, including angioedema

Metabolism and Nutrition Disorders
lactic acidosis, hypokalemia, hypophosphatemia

Respiratory, Thoracic, and Mediastinal Disorders
dyspnea

Gastrointestinal Disorders
pancreatitis, increased amylase, abdominal pain

Hepatobiliary Disorders
hepatic steatosis, hepatitis, increased liver enzymes (most commonly AST, ALT gamma GT)

Skin and Subcutaneous Tissue Disorders
rash

Musculoskeletal and Connective Tissue Disorders
rhabdomyolysis, osteomalacia (manifested as bone pain and which may contribute to fractures), muscular weakness, myopathy

Renal and Urinary Disorders
acute renal failure, renal failure, acute tubular necrosis, Fanconi syndrome, proximal renal tubulopathy, interstitial nephritis (including acute cases), nephrogenic diabetes insipidus, renal insufficiency, increased creatinine, proteinuria, polyuria

General Disorders and Administration Site Conditions
asthenia

The following adverse reactions, listed under the body system headings above, may occur as a consequence of proximal renal tubulopathy: rhabdomyolysis, osteomalacia, hypokalemia, muscular weakness, myopathy, hypophosphatemia.

7 DRUG INTERACTIONS

No drug interaction trials have been conducted using TRUVADA tablets. Drug interaction trials have been conducted with emtricitabine and tenofovir disoproxil fumarate, the components of TRUVADA. This section describes clinically relevant drug interactions observed with emtricitabine and tenofovir disoproxil fumarate [see Clinical Pharmacology (12.3)] .

7.1 Didanosine

Coadministration of TRUVADA and didanosine should be undertaken with caution and patients receiving this combination should be monitored closely for didanosine-associated adverse reactions. Didanosine should be discontinued in patients who develop didanosine-associated adverse reactions.

When tenofovir disoproxil fumarate was administered with didanosine the Cmax and AUC of didanosine increased significantly [see Clinical Pharmacology (12.3)] . The mechanism of this interaction is unknown. Higher didanosine concentrations could potentiate didanosine-associated adverse reactions, including pancreatitis, and neuropathy. Suppression of CD4+ cell counts has been observed in patients receiving tenofovir DF with didanosine 400 mg daily.

In patients weighing greater than 60 kg, the didanosine dose should be reduced to 250 mg when it is coadministered with TRUVADA. Data are not available to recommend a dose adjustment of didanosine for adult or pediatric patients weighing less than 60 kg. When coadministered, TRUVADA and Videx EC may be taken under fasted conditions or with a light meal (less than 400 kcal, 20% fat).

7.2 HIV-1 Protease Inhibitors

Tenofovir decreases the AUC and Cmin of atazanavir [see Clinical Pharmacology (12.3)] . When coadministered with TRUVADA, it is recommended that atazanavir 300 mg is given with ritonavir 100 mg. TRUVADA should not be coadministered with atazanavir without ritonavir .

Lopinavir/ritonavir, atazanavir coadministered with ritonavir, and darunavir coadministered with ritonavir have been shown to increase tenofovir concentrations [see Clinical Pharmacology (12.3)] . Tenofovir disoproxil fumarate is a substrate of P-glycoprotein (Pgp) and breast cancer resistance protein (BCRP) transporters. When tenofovir disoproxil fumarate is co-administered with an inhibitor of these transporters, an increase in absorption may be observed. Patients receiving TRUVADA concomitantly with lopinavir/ritonavir, ritonavir-boosted atazanavir, or ritonavir-boosted darunavir should be monitored for tenofovir disoproxil fumarate-associated adverse reactions. TRUVADA should be discontinued in patients who develop tenofovir disoproxil fumarate-associated adverse reactions .

7.3 Hepatitis C Antiviral Agents

Coadministration of tenofovir disoproxil fumarate and HARVONI® (ledipasvir/sofosbuvir) has been shown to increase tenofovir exposure [see Clinical Pharmacology (12.3)] .

In patients receiving TRUVADA concomitantly with HARVONI without an HIV-1 protease inhibitor/ritonavir or an HIV-1 protease inhibitor/cobicistat combination, monitor for adverse reactions associated with tenofovir disoproxil fumarate.

In patients receiving TRUVADA concomitantly with HARVONI and an HIV-1 protease inhibitor/ritonavir or an HIV-1 protease inhibitor/cobicistat combination, consider an alternative HCV or antiretroviral therapy, as the safety of increased tenofovir concentrations in this setting has not been established. If coadministration is necessary, monitor for adverse reactions associated with tenofovir disoproxil fumarate.

7.4 Drugs Affecting Renal Function

Emtricitabine and tenofovir are primarily excreted by the kidneys by a combination of glomerular filtration and active tubular secretion [see Clinical Pharmacology (12.3)] . No drug-drug interactions due to competition for renal excretion have been observed; however, coadministration of TRUVADA with drugs that are eliminated by active tubular secretion may increase concentrations of emtricitabine, tenofovir, and/or the coadministered drug. Some examples include, but are not limited to, acyclovir, adefovir dipivoxil, cidofovir, ganciclovir, valacyclovir, valganciclovir, aminoglycosides (e.g., gentamicin), and high-dose or multiple NSAIDs [see Warnings and Precautions (5.3)] . Drugs that decrease renal function may increase concentrations of emtricitabine and/or tenofovir.

8 USE IN SPECIFIC POPULATIONS

8.1 Pregnancy

Pregnancy Category B

Antiretroviral Pregnancy Registry: To monitor fetal outcomes of pregnant women exposed to TRUVADA, an Antiretroviral Pregnancy Registry (APR) has been established. Healthcare providers are encouraged to register patients by calling 1-800-258-4263.

Risk Summary

TRUVADA has been evaluated in a limited number of women during pregnancy and postpartum. Available human and animal data suggest that TRUVADA does not increase the risk of major birth defects overall compared to the background rate. There are, however, no adequate and well-controlled trials in pregnant women. Because the studies in humans cannot rule out the possibility of harm, TRUVADA should be used during pregnancy only if clearly needed. If an uninfected individual becomes pregnant while taking TRUVADA for a PrEP indication, careful consideration should be given to whether use of TRUVADA should be continued, taking into account the potential increased risk of HIV-1 infection during pregnancy.

Clinical Considerations

As of July 2011, the APR has received prospective reports of 764 and 1,219 exposures to emtricitabine- and tenofovir-containing regimens, respectively in the first trimester, 321 and 455 exposures, respectively, in second trimester, and 140 and 257 exposures, respectively, in the third trimester. Birth defects occurred in 18 of 764 (2.4%) live births for emtricitabine-containing regimens and 27 of 1219 (2.2%) live births for tenofovir-containing regimens (first trimester exposure) and 10 of 461 (2.2%) live births for emtricitabine-containing regimens and 15 of 714 (2.1%) live births for tenofovir-containing regimens (second/third trimester exposure). Among pregnant women in the U.S. reference population, the background rate of birth defects is 2.7%. There was no association between emtricitabine or tenofovir and overall birth defects observed in the APR.

Animal Data

Emtricitabine:

The incidence of fetal variations and malformations was not increased in embryofetal toxicity studies performed with emtricitabine in mice at exposures (AUC) approximately 60-fold higher and in rabbits at approximately 120-fold higher than human exposures at the recommended daily dose.

Tenofovir Disoproxil Fumarate:

Reproduction studies have been performed in rats and rabbits at doses up to 14 and 19 times the human dose based on body surface area comparisons and revealed no evidence of impaired fertility or harm to the fetus due to tenofovir.

8.3 Nursing Mothers

Nursing Mothers: The Centers for Disease Control and Prevention recommend that HIV-1 infected mothers not breast-feed their infants to avoid risking postnatal transmission of HIV-1.

Studies in humans have shown that both tenofovir and emtricitabine are excreted in human milk. Because the risks of low level exposure to emtricitabine and tenofovir to infants are unknown, mothers should be instructed not to breast-feed if they are receiving TRUVADA, whether they are taking TRUVADA for treatment or to reduce the risk of acquiring HIV-1 .

Emtricitabine

Samples of breast milk obtained from five HIV-1 infected mothers show that emtricitabine is secreted in human milk. Breastfeeding infants whose mothers are being treated with emtricitabine may be at risk for developing viral resistance to emtricitabine. Other emtricitabine-associated risks in infants breastfed by mothers being treated with emtricitabine are unknown.

Tenofovir Disoproxil Fumarate

Samples of breast milk obtained from five HIV-1 infected mothers show that tenofovir is secreted in human milk. Tenofovir-associated risks, including the risk of viral resistance to tenofovir, in infants breastfed by mothers being treated with tenofovir disoproxil fumarate are unknown.

8.4 Pediatric Use

No pediatric clinical trial was conducted to evaluate the safety and efficacy of TRUVADA. Data from previously conducted trials with the individual drug products, EMTRIVA and VIREAD, were relied upon to support dosing recommendations for TRUVADA. For additional information, consult the prescribing information for EMTRIVA and VIREAD.

TRUVADA should only be administered to HIV-1 infected pediatric patients with body weight greater than or equal to 17 kg and who are able to swallow a whole tablet. Because it is a fixed-dose combination tablet, TRUVADA cannot be adjusted for patients of lower weight [see Warnings and Precautions (5.5), Adverse Reactions (6.1) and Clinical Pharmacology (12.3)] . TRUVADA has not been evaluated for use in pediatric patients weighing less than 17 kg.

8.5 Geriatric Use

Clinical trials of EMTRIVA or VIREAD did not include sufficient numbers of subjects aged 65 and over to determine whether they respond differently from younger subjects. In general, dose selection for the elderly patients should be cautious, keeping in mind the greater frequency of decreased hepatic, renal, or cardiac function, and of concomitant disease or other drug therapy.

8.6 Patients with Impaired Renal Function

Treatment of HIV-1 Infection

The dosing interval for TRUVADA should be modified in HIV-infected adult patients with estimated creatinine clearance of 30–49 mL/min. TRUVADA should not be used in patients with estimated creatinine clearance below 30 mL/min and in patients with end-stage renal disease requiring dialysis [see Dosage and Administration (2.4)] .

Pre-exposure Prophylaxis

TRUVADA for a PrEP indication should not be used in HIV-1 uninfected individuals with estimated creatinine clearance below 60 mL/min. If a decrease in estimated creatinine clearance is observed in uninfected individuals while using TRUVADA for PrEP, evaluate potential causes and re-assess potential risks and benefits of continued use [see Dosage and Administration (2.4)] .

10 OVERDOSAGE

If overdose occurs, the patient must be monitored for evidence of toxicity, and standard supportive treatment applied as necessary.

Emtricitabine: Limited clinical experience is available at doses higher than the therapeutic dose of EMTRIVA. In one clinical pharmacology trial, single doses of emtricitabine 1200 mg were administered to 11 subjects. No severe adverse reactions were reported.

Hemodialysis treatment removes approximately 30% of the emtricitabine dose over a 3-hour dialysis period starting within 1.5 hours of emtricitabine dosing (blood flow rate of 400 mL/min and a dialysate flow rate of 600 mL/min). It is not known whether emtricitabine can be removed by peritoneal dialysis.

Tenofovir Disoproxil Fumarate: Limited clinical experience at doses higher than the therapeutic dose of VIREAD 300 mg is available. In one trial, 600 mg tenofovir disoproxil fumarate was administered to 8 subjects orally for 28 days, and no severe adverse reactions were reported. The effects of higher doses are not known.

Tenofovir is efficiently removed by hemodialysis with an extraction coefficient of approximately 54%. Following a single 300 mg dose of VIREAD, a four-hour hemodialysis session removed approximately 10% of the administered tenofovir dose.

11 DESCRIPTION

TRUVADA tablets are fixed-dose combination tablets containing emtricitabine and tenofovir disoproxil fumarate. Emtricitabine is a synthetic nucleoside analog of cytidine. Tenofovir DF is converted in vivo to tenofovir, an acyclic nucleoside phosphonate (nucleotide) analog of adenosine 5′-monophosphate. Both emtricitabine and tenofovir exhibit inhibitory activity against HIV-1 reverse transcriptase.

Emtricitabine: The chemical name of emtricitabine is 5-fluoro-1-(2 R,5 S)-[2-(hydroxymethyl)-1,3-oxathiolan-5-yl]cytosine. Emtricitabine is the (-) enantiomer of a thio analog of cytidine, which differs from other cytidine analogs in that it has a fluorine in the 5-position.

It has a molecular formula of C8H10FN3O3S and a molecular weight of 247.24. It has the following structural formula:

Emtricitabine is a white to off-white crystalline powder with a solubility of approximately 112 mg/mL in water at 25 °C. The partition coefficient (log p) for emtricitabine is -0.43 and the pKa is 2.65.

Tenofovir Disoproxil Fumarate: Tenofovir disoproxil fumarate is a fumaric acid salt of the bis-isopropoxycarbonyloxymethyl ester derivative of tenofovir. The chemical name of tenofovir disoproxil fumarate is 9-[(R)-2 [[bis[[(isopropoxycarbonyl)oxy]-methoxy]phosphinyl]methoxy]propyl]adenine fumarate (1:1). It has a molecular formula of C19H30N5O10P ∙ C4H4O4 and a molecular weight of 635.52. It has the following structural formula:

Tenofovir disoproxil fumarate is a white to off-white crystalline powder with a solubility of 13.4 mg/mL in water at 25 °C. The partition coefficient (log p) for tenofovir disoproxil is 1.25 and the pKa is 3.75. All dosages are expressed in terms of tenofovir disoproxil fumarate except where otherwise noted.

TRUVADA tablets are for oral administration, and are available in the following strengths:

- Film-coated tablet containing 200 mg of emtricitabine and 300 mg of tenofovir disoproxil fumarate (which is equivalent to 245 mg of tenofovir disoproxil) as active ingredients
- Film-coated tablet containing 167 mg of emtricitabine and 250 mg of tenofovir disoproxil fumarate (which is equivalent to 204 mg of tenofovir disoproxil) as active ingredients
- Film-coated tablet containing 133 mg of emtricitabine and 200 mg of tenofovir disoproxil fumarate (which is equivalent to 163 mg of tenofovir disoproxil) as active ingredients
- Film-coated tablet containing 100 mg of emtricitabine and 150 mg of tenofovir disoproxil fumarate (which is equivalent to 123 mg of tenofovir disoproxil) as active ingredients

All strength of TRUVADA tablets also include the following inactive ingredients: croscarmellose sodium, lactose monohydrate, magnesium stearate, microcrystalline cellulose, and pregelatinized starch (gluten free). The 200 mg/300 mg strength tablets are coated with Opadry II Blue Y-30-10701, which contains FD&C Blue #2 aluminum lake, hypromellose 2910, lactose monohydrate, titanium dioxide, and triacetin. The 167 mg/250 mg, 133 mg/200 mg, and 100 mg/150 mg strength tablets are coated with Opadry II Blue, which contains FD&C Blue #2 aluminum lake, hypromellose 2910, lactose monohydrate, titanium dioxide, and triacetin.

12 CLINICAL PHARMACOLOGY

For additional information on Mechanism of Action, Antiviral Activity, Resistance and Cross Resistance, consult the EMTRIVA and VIREAD prescribing information.

12.1 Mechanism of Action

TRUVADA is a fixed-dose combination of antiviral drugs emtricitabine and tenofovir disoproxil fumarate [see Microbiology (12.4)].

12.3 Pharmacokinetics

TRUVADA: One TRUVADA tablet was bioequivalent to one EMTRIVA capsule (200 mg) plus one VIREAD tablet (300 mg) following single-dose administration to fasting healthy subjects (N=39).

Emtricitabine: The pharmacokinetic properties of emtricitabine are summarized in Table 7. Following oral administration of EMTRIVA, emtricitabine is rapidly absorbed with peak plasma concentrations occurring at 1–2 hours post-dose. Less than 4% of emtricitabine binds to human plasma proteins in vitro and the binding is independent of concentration over the range of 0.02–200 µg/mL. Following administration of radiolabelled emtricitabine, approximately 86% is recovered in the urine and 13% is recovered as metabolites. The metabolites of emtricitabine include 3′-sulfoxide diastereomers and their glucuronic acid conjugate. Emtricitabine is eliminated by a combination of glomerular filtration and active tubular secretion. Following a single oral dose of EMTRIVA, the plasma emtricitabine half-life is approximately 10 hours.

Tenofovir Disoproxil Fumarate: The pharmacokinetic properties of tenofovir disoproxil fumarate are summarized in Table 7. Following oral administration of VIREAD, maximum tenofovir serum concentrations are achieved in 1.0 ± 0.4 hour. Less than 0.7% of tenofovir binds to human plasma proteins in vitro and the binding is independent of concentration over the range of 0.01–25 µg/mL. Approximately 70–80% of the intravenous dose of tenofovir is recovered as unchanged drug in the urine. Tenofovir is eliminated by a combination of glomerular filtration and active tubular secretion. Following a single oral dose of VIREAD, the terminal elimination half-life of tenofovir is approximately 17 hours.

Table 7 Single Dose Pharmacokinetic Parameters for Emtricitabine and Tenofovir in Adults [NC=Not calculated]
 | Emtricitabine | Tenofovir
Fasted Oral Bioavailability [Median (range)] (%) | 92 (83.1–106.4) | 25 (NC–45.0)
Plasma Terminal Elimination Half-Life (hr) | 10 (7.4–18.0) | 17 (12.0–25.7)
Cmax [Mean (± SD)] (μg/mL) | 1.8±0.72 [Data presented as steady state values] | 0.30±0.09
AUC (μg ∙hr/mL) | 10.0±3.12 | 2.29±0.69
CL/F (mL/min) | 302±94 | 1043±115
CLrenal (mL/min) | 213±89 | 243±33

Effects of Food on Oral Absorption

TRUVADA may be administered with or without food. Administration of TRUVADA following a high fat meal (784 kcal; 49 grams of fat) or a light meal (373 kcal; 8 grams of fat) delayed the time of tenofovir Cmax by approximately 0.75 hour. The mean increases in tenofovir AUC and Cmax were approximately 35% and 15%, respectively, when administered with a high fat or light meal, compared to administration in the fasted state. In previous safety and efficacy trials, VIREAD (tenofovir) was taken under fed conditions. Emtricitabine systemic exposures (AUC and Cmax) were unaffected when TRUVADA was administered with either a high fat or a light meal.

Special Populations

Race

Emtricitabine: No pharmacokinetic differences due to race have been identified following the administration of EMTRIVA.

Tenofovir Disoproxil Fumarate: There were insufficient numbers from racial and ethnic groups other than Caucasian to adequately determine potential pharmacokinetic differences among these populations following the administration of VIREAD.

Gender

Emtricitabine and Tenofovir Disoproxil Fumarate: Emtricitabine and tenofovir pharmacokinetics are similar in male and female subjects.

Pediatric Patients

The pharmacokinetic data for tenofovir and emtricitabine following administration of TRUVADA in pediatric subjects weighing 17 kg and above are not available. The dosing recommendations of TRUVADA in this population are based on the dosing recommendations of EMTRIVA and VIREAD in this population. Refer to the EMTRIVA and VIREAD prescribing information for pharmacokinetic information on the individual products in pediatric patients.

TRUVADA should not be administered to HIV-1 infected pediatric patients weighing less than 17 kg.

Geriatric Patients

Pharmacokinetics of emtricitabine and tenofovir have not been fully evaluated in the elderly (65 years of age and older).

Patients with Impaired Renal Function

The pharmacokinetics of emtricitabine and tenofovir are altered in subjects with renal impairment [see Warnings and Precautions (5.3)] . In adult subjects with creatinine clearance below 50 mL/min, Cmax, and AUC0–∞ of emtricitabine and tenofovir were increased. It is recommended that the dosing interval for TRUVADA be modified in HIV-infected adult patients with estimated creatinine clearance 30–49 mL/min. No data are available to make dose recommendations in pediatric patients with renal impairment. TRUVADA should not be used in patients with estimated creatinine clearance below 30 mL/min and in patients with end-stage renal disease requiring dialysis [see Dosage and Administration (2.4)] .

TRUVADA for a PrEP indication should not be used in HIV-1 uninfected individuals with estimated creatinine clearance below 60 mL/min. If a decrease in estimated creatinine clearance is observed in uninfected individuals while using TRUVADA for PrEP, evaluate potential causes and re-assess potential risks and benefits of continued use [see Dosage and Administration (2.4)] .

Patients with Hepatic Impairment

The pharmacokinetics of tenofovir following a 300 mg dose of VIREAD have been studied in non-HIV infected subjects with moderate to severe hepatic impairment. There were no substantial alterations in tenofovir pharmacokinetics in subjects with hepatic impairment compared with unimpaired subjects. The pharmacokinetics of TRUVADA or emtricitabine have not been studied in subjects with hepatic impairment; however, emtricitabine is not significantly metabolized by liver enzymes, so the impact of liver impairment should be limited.

Assessment of Drug Interactions

The steady state pharmacokinetics of emtricitabine and tenofovir were unaffected when emtricitabine and tenofovir disoproxil fumarate were administered together versus each agent dosed alone.

In vitro studies and clinical pharmacokinetic drug-drug interaction trials have shown that the potential for CYP mediated interactions involving emtricitabine and tenofovir with other medicinal products is low.

No clinically significant drug interactions have been observed between emtricitabine and famciclovir, indinavir, stavudine, tenofovir disoproxil fumarate, and zidovudine (see Tables 8 and 9). Similarly, no clinically significant drug interactions have been observed between tenofovir disoproxil fumarate and efavirenz, methadone, nelfinavir, oral contraceptives, ribavirin, or sofosbuvir in trials conducted in healthy volunteers (see Tables 10 and 11).

Table 8 Drug Interactions: Changes in Pharmacokinetic Parameters for Emtricitabine in the Presence of the Coadministered Drug [All interaction trials conducted in healthy volunteers]
Coadministered Drug | Dose of Coadministered Drug (mg) | Emtricitabine Dose (mg) | N | % Change of Emtricitabine Pharmacokinetic Parameters [↑ = Increase; ↓ = Decrease; ⇔ = No Effect; NA = Not Applicable] (90% CI)
Coadministered Drug | Dose of Coadministered Drug (mg) | Emtricitabine Dose (mg) | N | Cmax | AUC | Cmin
Tenofovir DF | 300 once daily × 7 days | 200 once daily × 7 days | 17 | ⇔ | ⇔ | ↑ 20 (↑ 12 to ↑ 29)
Zidovudine | 300 twice daily × 7 days | 200 once daily × 7 days | 27 | ⇔ | ⇔ | ⇔
Indinavir | 800 × 1 | 200 × 1 | 12 | ⇔ | ⇔ | NA
Famciclovir | 500 × 1 | 200 × 1 | 12 | ⇔ | ⇔ | NA
Stavudine | 40 × 1 | 200 × 1 | 6 | ⇔ | ⇔ | NA

Table 9 Drug Interactions: Changes in Pharmacokinetic Parameters for Coadministered Drug in the Presence of Emtricitabine [All interaction trials conducted in healthy volunteers]
Coadministered Drug | Dose of Coadministered Drug (mg) | Emtricitabine Dose (mg) | N | % Change of Coadministered Drug Pharmacokinetic Parameters [↑ = Increase; ↓ = Decrease; ⇔ = No Effect; NA = Not Applicable] (90% CI)
Coadministered Drug | Dose of Coadministered Drug (mg) | Emtricitabine Dose (mg) | N | Cmax | AUC | Cmin
Tenofovir DF | 300 once daily × 7 days | 200 once daily × 7 days | 17 | ⇔ | ⇔ | ⇔
Zidovudine | 300 twice daily × 7 days | 200 once daily × 7 days | 27 | ↑ 17 (↑ 0 to ↑ 38) | ↑ 13 (↑ 5 to ↑ 20) | ⇔
Indinavir | 800 × 1 | 200 × 1 | 12 | ⇔ | ⇔ | NA
Famciclovir | 500 × 1 | 200 × 1 | 12 | ⇔ | ⇔ | NA
Stavudine | 40 × 1 | 200 × 1 | 6 | ⇔ | ⇔ | NA

Table 10 Drug Interactions: Changes in Pharmacokinetic Parameters for Tenofovir [Subjects received VIREAD 300 mg once daily] in the Presence of the Coadministered Drug
Coadministered Drug | Dose of Coadministered Drug (mg) | N | % Change of Tenofovir Pharmacokinetic Parameters [Increase = ↑; Decrease = ↓; No Effect = ⇔; NC = Not Calculated] (90% CI)
Coadministered Drug | Dose of Coadministered Drug (mg) | N | Cmax | AUC | Cmin
Atazanavir [Reyataz Prescribing Information] | 400 once daily × 14 days | 33 | ↑ 14 (↑ 8 to ↑ 20) | ↑ 24 (↑ 21 to ↑ 28) | ↑ 22 (↑ 15 to ↑ 30)
Atazanavir/Ritonavir | 300/100 once daily | 12 | ↑ 34 (↑ 20 to ↑ 51) | ↑ 37 (↑ 30 to ↑ 45) | ↑ 29 (↑ 21 to ↑ 36)
Darunavir/Ritonavir [Prezista Prescribing Information] | 300/100 twice daily | 12 | ↑ 24 (↑ 8 to ↑ 42) | ↑ 22 (↑ 10 to ↑ 35) | ↑ 37 (↑ 19 to ↑ 57)
Indinavir | 800 three times daily × 7 days | 13 | ↑ 14 (↓ 3 to ↑ 33) | ⇔ | ⇔
Ledipasvir/Sofosbuvir [Data generated from simultaneous dosing with HARVONI (ledipasvir/sofosbuvir). Staggered administration (12 hours apart) provided similar results.] , [Comparison based on exposures when administered as atazanavir/ritonavir + emtricitabine/tenofovir DF.] | 90/400 once daily ×10 days | 24 | ↑ 47 (↑ 37 to ↑ 58) | ↑ 35 (↑ 29 to ↑42) | ↑ 47 (↑ 38 to ↑ 57)
Ledipasvir/Sofosbuvir , [Comparison based on exposures when administered as darunavir/ritonavir + emtricitabine/tenofovir DF.] | 90/400 once daily ×10 days | 23 | ↑ 64 (↑ 54 to ↑ 74) | ↑ 50 (↑ 42 to ↑ 59) | ↑ 59 (↑ 49 to ↑ 70)
Ledipasvir/Sofosbuvir [Study conducted with ATRIPLA (efavirenz/emtricitabine/tenofovir DF) coadministered with HARVONI.] | 90/400 once daily ×14 days | 15 | ↑ 79 (↑ 56 to ↑ 104) | ↑ 98 (↑ 77 to ↑ 123) | ↑ 163 (↑ 132 to ↑ 197)
Ledipasvir/Sofosbuvir [Study conducted with COMPLERA (emtricitabine/rilpivirine/tenofovir DF) coadministered with HARVONI.] | 90/400 once daily ×10 days | 14 | ↑ 32 (↑ 25 to ↑ 39) | ↑ 40 (↑ 31 to ↑ 50) | ↑ 91 (↑ 74 to ↑ 110)
Lopinavir/Ritonavir | 400/100 twice daily × 14 days | 24 | ⇔ | ↑ 32 (↑ 25 to ↑ 38) | ↑ 51 (↑ 37 to ↑ 66)
Saquinavir/Ritonavir | 1000/100 twice daily × 14 days | 35 | ⇔ | ⇔ | ↑ 23 (↑ 16 to ↑ 30)
Sofosbuvir [Study conducted with ATRIPLA coadministered with SOVALDI ® (sofosbuvir).] | 400 single dose | 16 | ↑ 25 (↑ 8 to ↑ 45) | ⇔ | ⇔
Tacrolimus | 0.05 mg/kg twice daily × 7 days | 21 | ↑ 13 (↑ 1 to ↑ 27) | ⇔ | ⇔
Tipranavir/Ritonavir [Aptivus Prescribing Information.] | 500/100 twice daily | 22 | ↓ 23 (↓ 32 to ↓ 13) | ↓ 2 (↓ 9 to ↑ 5) | ↑ 7 (↓ 2 to ↑ 17)
Tipranavir/Ritonavir [Aptivus Prescribing Information.] | 750/200 twice daily (23 doses) | 20 | ↓ 38 (↓ 46 to ↓ 29) | ↑ 2 (↓ 6 to ↑ 10) | ↑ 14 (↑ 1 to ↑ 27)

No effect on the pharmacokinetic parameters of the following coadministered drugs was observed with TRUVADA: abacavir, didanosine (buffered tablets), emtricitabine, entecavir and lamivudine.

Table 11 Drug Interactions: Changes in Pharmacokinetic Parameters for Coadministered Drug in the Presence of Tenofovir
Coadministered Drug | Dose of Coadministered Drug (mg) | N | % Change of Coadministered Drug Pharmacokinetic Parameters [Increase = ↑; Decrease = ↓; No Effect = ⇔; NA = Not Applicable] (90% CI)
Coadministered Drug | Dose of Coadministered Drug (mg) | N | Cmax | AUC | Cmin
Abacavir | 300 once | 8 | ↑ 12 (↓ 1 to ↑ 26) | ⇔ | NA
Atazanavir [Reyataz Prescribing Information] | 400 once daily × 14 days | 34 | ↓ 21 (↓ 27 to ↓ 14) | ↓ 25 (↓ 30 to ↓ 19) | ↓ 40 (↓ 48 to ↓ 32)
Atazanavir | Atazanavir/Ritonavir 300/100 once daily × 42 days | 10 | ↓ 28 (↓ 50 to ↑ 5) | ↓ 25 [In HIV-infected subjects, addition of tenofovir DF to atazanavir 300 mg plus ritonavir 100 mg, resulted in AUC and C min values of atazanavir that were 2.3 and 4-fold higher than the respective values observed for atazanavir 400 mg when given alone.] (↓ 42 to ↓ 3) | ↓ 23 (↓ 46 to ↑ 10)
Darunavir [Prezista Prescribing Information.] | Darunavir/Ritonavir 300/100 once daily | 12 | ↑ 16 (↓ 6 to ↑ 42) | ↑ 21 (↓ 5 to ↑ 54) | ↑ 24 (↓ 10 to ↑ 69)
Didanosine [Videx EC Prescribing Information. Subjects received didanosine enteric-coated capsules.] | 250 once, simultaneously with tenofovir DF and a light meal [373 kcal, 8.2 g fat] | 33 | ↓ 20 [Compared with didanosine (enteric-coated) 400 mg administered alone under fasting conditions.] (↓ 32 to ↓ 7) | ⇔ | NA
Emtricitabine | 200 once daily × 7 days | 17 | ⇔ | ⇔ | ↑ 20 (↑ 12 to ↑ 29)
Indinavir | 800 three times daily × 7 days | 12 | ↓ 11 (↓ 30 to ↑ 12) | ⇔ | ⇔
Entecavir | 1 once daily × 10 days | 28 | ⇔ | ↑ 13 (↑ 11 to ↑ 15) | ⇔
Lamivudine | 150 twice daily × 7 days | 15 | ↓ 24 (↓ 34 to ↓ 12) | ⇔ | ⇔
Lopinavir Ritonavir | Lopinavir/Ritonavir 400/100 twice daily × 14 days | 24 | ⇔ ⇔ | ⇔ ⇔ | ⇔ ⇔
Saquinavir | Saquinavir/Ritonavir 1000/100 twice daily × 14 days | 32 | ↑ 22 (↑ 6 to ↑41) | ↑ 29 [Increases in AUC and C min are not expected to be clinically relevant; hence no dose adjustments are required when tenofovir DF and ritonavir-boosted saquinavir are coadministered.] (↑ 12 to ↑ 48) | ↑ 47 (↑ 23 to ↑ 76)
Ritonavir | Saquinavir/Ritonavir 1000/100 twice daily × 14 days | 32 | ⇔ | ⇔ | ↑ 23 (↑ 3 to ↑ 46)
Tacrolimus | 0.05 mg/kg twice daily × 7 days | 21 | ⇔ | ⇔ | ⇔
Tipranavir [Aptivus Prescribing Information.] | Tipranavir/Ritonavir 500/100 twice daily | 22 | ↓ 17 (↓ 26 to ↓ 6) | ↓ 18 (↓ 25 to ↓ 9) | ↓ 21 (↓ 30 to ↓ 10)
Tipranavir [Aptivus Prescribing Information.] | Tipranavir/Ritonavir 750/200 twice daily (23 doses) | 20 | ↓ 11 (↓ 16 to ↓ 4) | ↓ 9 (↓ 15 to ↓ 3) | ↓ 12 (↓ 22 to 0)

Coadministration of tenofovir disoproxil fumarate with didanosine results in changes in the pharmacokinetics of didanosine that may be of clinical significance. Concomitant dosing of tenofovir disoproxil fumarate with didanosine enteric-coated capsules significantly increases the Cmax and AUC of didanosine. When didanosine 250 mg enteric-coated capsules were administered with tenofovir disoproxil fumarate, systemic exposures of didanosine were similar to those seen with the 400 mg enteric-coated capsules alone under fasted conditions. The mechanism of this interaction is unknown. See Drug Interactions (7.1) regarding use of didanosine with VIREAD.

12.4 Microbiology

Mechanism of Action

Emtricitabine: Emtricitabine, a synthetic nucleoside analog of cytidine, is phosphorylated by cellular enzymes to form emtricitabine 5'-triphosphate. Emtricitabine 5'-triphosphate inhibits the activity of the HIV-1 reverse transcriptase (RT) by competing with the natural substrate deoxycytidine 5'-triphosphate and by being incorporated into nascent viral DNA which results in chain termination. Emtricitabine 5′-triphosphate is a weak inhibitor of mammalian DNA polymerase α, β, ε and mitochondrial DNA polymerase γ.

Tenofovir Disoproxil Fumarate: Tenofovir disoproxil fumarate is an acyclic nucleoside phosphonate diester analog of adenosine monophosphate. Tenofovir disoproxil fumarate requires initial diester hydrolysis for conversion to tenofovir and subsequent phosphorylations by cellular enzymes to form tenofovir diphosphate. Tenofovir diphosphate inhibits the activity of HIV-1 RT by competing with the natural substrate deoxyadenosine 5′-triphosphate and, after incorporation into DNA, by DNA chain termination. Tenofovir diphosphate is a weak inhibitor of mammalian DNA polymerases α, β, and mitochondrial DNA polymerase γ.

Antiviral Activity

Emtricitabine and Tenofovir Disoproxil Fumarate: No antagonism was observed in combination studies evaluating the cell culture antiviral activity of emtricitabine and tenofovir together.

Emtricitabine: The antiviral activity of emtricitabine against laboratory and clinical isolates of HIV-1 was assessed in lymphoblastoid cell lines, the MAGI-CCR5 cell line, and peripheral blood mononuclear cells. The 50% effective concentration (EC50) values for emtricitabine were in the range of 0.0013–0.64 µM (0.0003–0.158 µg/mL). In drug combination studies of emtricitabine with nucleoside reverse transcriptase inhibitors (abacavir, lamivudine, stavudine, zidovudine), non-nucleoside reverse transcriptase inhibitors (delavirdine, efavirenz, nevirapine), and protease inhibitors (amprenavir, nelfinavir, ritonavir, saquinavir), no antagonism was observed. Emtricitabine displayed antiviral activity in cell culture against HIV-1 clades A, B, C, D, E, F, and G (EC50 values ranged from 0.007–0.075 µM) and showed strain specific activity against HIV-2 (EC50 values ranged from 0.007–1.5 µM).

Tenofovir Disoproxil Fumarate: The antiviral activity of tenofovir against laboratory and clinical isolates of HIV-1 was assessed in lymphoblastoid cell lines, primary monocyte/macrophage cells and peripheral blood lymphocytes. The EC50 values for tenofovir were in the range of 0.04–8.5 µM. In drug combination studies of tenofovir with nucleoside reverse transcriptase inhibitors (abacavir, didanosine, lamivudine, stavudine, zidovudine), non-nucleoside reverse transcriptase inhibitors (delavirdine, efavirenz, nevirapine), and protease inhibitors (amprenavir, indinavir, nelfinavir, ritonavir, saquinavir), no antagonism was observed. Tenofovir displayed antiviral activity in cell culture against HIV-1 clades A, B, C, D, E, F, G and O (EC50 values ranged from 0.5–2.2 µM) and showed strain specific activity against HIV-2 (EC50 values ranged from 1.6 µM to 5.5 µM).

Prophylactic Activity in a Nonhuman Primate Model of HIV Transmission

Emtricitabine and Tenofovir Disoproxil Fumarate: The prophylactic activity of the combination of daily oral emtricitabine (FTC) and tenofovir disoproxil fumarate (TDF) was evaluated in a controlled study of macaques inoculated once weekly for 14 weeks with SIV/HIV-1 chimeric virus (SHIV) applied to the rectal surface. Of the 18 control animals, 17 became infected after a median of 2 weeks. In contrast, 4 of the 6 animals treated daily with oral FTC and TDF remained uninfected and the two infections that did occur were significantly delayed until 9 and 12 weeks and exhibited reduced viremia. An M184I-expressing FTC-resistant variant emerged in 1 of the 2 macaques after 3 weeks of continued drug exposure.

Resistance

Emtricitabine and Tenofovir Disoproxil Fumarate: HIV-1 isolates with reduced susceptibility to the combination of emtricitabine and tenofovir have been selected in cell culture. Genotypic analysis of these isolates identified the M184V/I and/or K65R amino acid substitutions in the viral RT. In addition, a K70E substitution in HIV-1 reverse transcriptase has been selected by tenofovir and results in reduced susceptibility to tenofovir.

In a clinical trial of treatment-naïve subjects [Study 934, see Clinical Studies (14.1)] , resistance analysis was performed on HIV-1 isolates from all confirmed virologic failure subjects with greater than 400 copies/mL of HIV-1 RNA at Week 144 or early discontinuation. Development of efavirenz resistance-associated substitutions occurred most frequently and was similar between the treatment arms. The M184V amino acid substitution, associated with resistance to EMTRIVA and lamivudine, was observed in 2/19 analyzed subject isolates in the EMTRIVA + VIREAD group and in 10/29 analyzed subject isolates in the zidovudine/lamivudine group. Through 144 weeks of Study 934, no subjects have developed a detectable K65R or K70E substitution in their HIV-1 as analyzed through standard genotypic analysis.

Emtricitabine: Emtricitabine-resistant isolates of HIV-1 have been selected in cell culture and in vivo. Genotypic analysis of these isolates showed that the reduced susceptibility to emtricitabine was associated with a substitution in the HIV-1 RT gene at codon 184 which resulted in an amino acid substitution of methionine by valine or isoleucine (M184V/I).

Tenofovir Disoproxil Fumarate: HIV-1 isolates with reduced susceptibility to tenofovir have been selected in cell culture. These viruses expressed a K65R substitution in RT and showed a 2–4 fold reduction in susceptibility to tenofovir.

In treatment-naïve subjects, isolates from 8/47 (17%) analyzed subjects developed the K65R substitution in the VIREAD arm through 144 weeks; 7 occurred in the first 48 weeks of treatment and 1 at Week 96. In treatment-experienced subjects, 14/304 (5%) isolates from subjects failing VIREAD through Week 96 showed greater than 1.4 fold (median 2.7) reduced susceptibility to tenofovir. Genotypic analysis of the resistant isolates showed a K65R amino acid substitution in the HIV-1 RT.

iPrEx Trial: In a clinical study of HIV-1 seronegative subjects [iPrEx Trial, see Clinical Studies (14.2)] , no amino acid substitutions associated with resistance to emtricitabine or tenofovir were detected at the time of seroconversion among 48 subjects in the TRUVADA group and 83 subjects in the placebo group who became infected with HIV-1 during the trial. Ten subjects were observed to be HIV-1 infected at time of enrollment. The M184V/I substitutions associated with resistance to emtricitabine were observed in 3 of the 10 subjects (2 of 2 in the TRUVADA group and 1 of 8 in the placebo group). One of the two subjects in the TRUVADA group harbored wild type virus at enrollment and developed the M184V substitution 4 weeks after enrollment. The other subject had indeterminate resistance at enrollment but was found to have the M184I substitution 4 weeks after enrollment.

Partners PrEP Trial: In a clinical study of HIV-1 seronegative subjects [Partners PrEP Trial, see Clinical Studies (14.3)], no variants expressing amino acid substitutions associated with resistance to emtricitabine or tenofovir were detected at the time of seroconversion among 12 subjects in the TRUVADA group, 15 subjects in the VIREAD group, and 51 subjects in the placebo group. Fourteen subjects were observed to be HIV-1 infected at the time of enrollment (3 in the TRUVADA group, 5 in the VIREAD group, and 6 in the placebo group). One of the three subjects in the TRUVADA group who was infected with wild type virus at enrollment selected an M184V expressing virus by week 12. Two of the five subjects in the VIREAD group had tenofovir-resistant viruses at the time of seroconversion; one subject infected with wild type virus at enrollment developed a K65R substitution by week 16, while the second subject had virus expressing the combination of D67N and K70R substitutions upon seroconversion at week 60, although baseline virus was not genotyped and it is unclear if the resistance emerged or was transmitted. Following enrollment, 4 subjects (2 in the VIREAD group, 1 in the TRUVADA group, and 1 in the placebo group) had virus expressing K103N or V106A substitutions, which confer high-level resistance to NNRTIs but have not been associated with tenofovir or emtricitabine and may have been present in the infecting virus.

Cross Resistance

Emtricitabine and Tenofovir Disoproxil Fumarate: Cross-resistance among certain nucleoside reverse transcriptase inhibitors (NRTIs) has been recognized. The M184V/I and/or K65R substitutions selected in cell culture by the combination of emtricitabine and tenofovir are also observed in some HIV-1 isolates from subjects failing treatment with tenofovir in combination with either emtricitabine or lamivudine, and either abacavir or didanosine. Therefore, cross-resistance among these drugs may occur in patients whose virus harbors either or both of these amino acid substitutions.

Emtricitabine: Emtricitabine-resistant isolates (M184V/I) were cross-resistant to lamivudine but retained susceptibility in cell culture to the NRTIs didanosine, stavudine, tenofovir, and zidovudine, and to NNRTIs (delavirdine, efavirenz, and nevirapine). HIV-1 isolates containing the K65R substitution, selected in vivo by abacavir, didanosine, and tenofovir, demonstrated reduced susceptibility to inhibition by emtricitabine. Viruses harboring substitutions conferring reduced susceptibility to stavudine and zidovudine (M41L, D67N, K70R, L210W, T215Y/F, K219Q/E), or didanosine (L74V) remained sensitive to emtricitabine. HIV-1 containing the K103N substitution associated with resistance to NNRTIs was susceptible to emtricitabine.

Tenofovir Disoproxil Fumarate: The K65R and K70E substitutions selected by tenofovir are also selected in some HIV-1-infected patients treated with abacavir or didanosine. HIV-1 isolates with the K65R and K70E substitutions also showed reduced susceptibility to emtricitabine and lamivudine. Therefore, cross-resistance among these NRTIs may occur in patients whose virus harbors the K65R or K70E substitutions. HIV-1 isolates from subjects (N=20) whose HIV-1 expressed a mean of 3 zidovudine-associated RT amino acid substitutions (M41L, D67N, K70R, L210W, T215Y/F, or K219Q/E/N) showed a 3.1-fold decrease in the susceptibility to tenofovir. Subjects whose virus expressed an L74V substitution without zidovudine resistance-associated substitutions (N=8) had reduced response to VIREAD. Limited data are available for patients whose virus expressed a Y115F substitution (N=3), Q151M substitution (N=2), or T69 insertion (N=4), all of whom had a reduced response.

13 NONCLINICAL TOXICOLOGY

13.1 Carcinogenesis, Mutagenesis, Impairment of Fertility

Emtricitabine: In long-term oral carcinogenicity studies of emtricitabine, no drug-related increases in tumor incidence were found in mice at doses up to 750 mg/kg/day (26 times the human systemic exposure at the therapeutic dose of 200 mg/day) or in rats at doses up to 600 mg/kg/day (31 times the human systemic exposure at the therapeutic dose).

Emtricitabine was not genotoxic in the reverse mutation bacterial test (Ames test), mouse lymphoma or mouse micronucleus assays.

Emtricitabine did not affect fertility in male rats at approximately 140-fold or in male and female mice at approximately 60-fold higher exposures (AUC) than in humans given the recommended 200 mg daily dose. Fertility was normal in the offspring of mice exposed daily from before birth (in utero) through sexual maturity at daily exposures (AUC) of approximately 60-fold higher than human exposures at the recommended 200 mg daily dose.

Tenofovir Disoproxil Fumarate: Long-term oral carcinogenicity studies of tenofovir disoproxil fumarate in mice and rats were carried out at exposures up to approximately 16 times (mice) and 5 times (rats) those observed in humans at the therapeutic dose for HIV-1 infection. At the high dose in female mice, liver adenomas were increased at exposures 16 times that in humans. In rats, the study was negative for carcinogenic findings at exposures up to 5 times that observed in humans at the therapeutic dose.

Tenofovir disoproxil fumarate was mutagenic in the in vitro mouse lymphoma assay and negative in an in vitro bacterial mutagenicity test (Ames test). In an in vivo mouse micronucleus assay, tenofovir disoproxil fumarate was negative when administered to male mice.

There were no effects on fertility, mating performance or early embryonic development when tenofovir disoproxil fumarate was administered to male rats at a dose equivalent to 10 times the human dose based on body surface area comparisons for 28 days prior to mating and to female rats for 15 days prior to mating through day seven of gestation. There was, however, an alteration of the estrous cycle in female rats.

13.2 Animal Toxicology and/or Pharmacology

Tenofovir and tenofovir disoproxil fumarate administered in toxicology studies to rats, dogs and monkeys at exposures (based on AUCs) greater than or equal to 6-fold those observed in humans caused bone toxicity. In monkeys the bone toxicity was diagnosed as osteomalacia. Osteomalacia observed in monkeys appeared to be reversible upon dose reduction or discontinuation of tenofovir. In rats and dogs, the bone toxicity manifested as reduced bone mineral density. The mechanism(s) underlying bone toxicity is unknown.

Evidence of renal toxicity was noted in four animal species. Increases in serum creatinine, BUN, glycosuria, proteinuria, phosphaturia, and/or calciuria and decreases in serum phosphate were observed to varying degrees in these animals. These toxicities were noted at exposures (based on AUCs) 2–20 times higher than those observed in humans. The relationship of the renal abnormalities, particularly the phosphaturia, to the bone toxicity is not known.

14 CLINICAL STUDIES

Clinical Study 934 supports the use of TRUVADA tablets for the treatment of HIV-1 infection. Additional data in support of the use of TRUVADA are derived from clinical Study 903, in which lamivudine and tenofovir disoproxil fumarate (tenofovir DF) were used in combination in treatment-naïve adults, and clinical Study 303 in which emtricitabine and lamivudine demonstrated comparable efficacy, safety and resistance patterns as part of multidrug regimens. For additional information about these trials, consult the prescribing information for tenofovir DF and emtricitabine. The iPrEx study and Partners PrEP study support the use of TRUVADA to help reduce the risk of acquiring HIV-1.

14.1 Study 934

Data through 144 weeks are reported for Study 934, a randomized, open-label, active-controlled multicenter trial comparing emtricitabine + tenofovir DF administered in combination with efavirenz versus zidovudine/lamivudine fixed-dose combination administered in combination with efavirenz in 511 antiretroviral-naïve subjects. From Weeks 96 to 144 of the trial, subjects received TRUVADA with efavirenz in place of emtricitabine + tenofovir DF with efavirenz. Subjects had a mean age of 38 years (range 18–80), 86% were male, 59% were Caucasian and 23% were Black. The mean baseline CD4+ cell count was 245 cells/mm^3 (range 2–1191) and median baseline plasma HIV-1 RNA was 5.01 log10 copies/mL (range 3.56–6.54). Subjects were stratified by baseline CD4+ cell count (< or ≥200 cells/mm^3); 41% had CD4+ cell counts <200 cells/mm^3 and 51% of subjects had baseline viral loads >100,000 copies/mL. Treatment outcomes through 48 and 144 weeks for those subjects who did not have efavirenz resistance at baseline are presented in Table 12.

Table 12 Outcomes of Randomized Treatment at Week 48 and 144 (Study 934)
Outcomes | At Week 48 |  | At Week 144
Outcomes | FTC + TDF + EFV (N=244) | AZT/3TC + EFV (N=243) | FTC + TDF + EFV (N=227) [Subjects who were responders at Week 48 or Week 96 (HIV-1 RNA <400 copies/mL) but did not consent to continue trial after Week 48 or Week 96 were excluded from analysis.] | AZT/3TC + EFV (N=229)
Responder [Subjects achieved and maintained confirmed HIV-1 RNA <400 copies/mL through Weeks 48 and 144.] | 84% | 73% | 71% | 58%
Virologic failure [Includes confirmed viral rebound and failure to achieve confirmed <400 copies/mL through Weeks 48 and 144.] | 2% | 4% | 3% | 6%
Rebound | 1% | 3% | 2% | 5%
Never suppressed | 0% | 0% | 0% | 0%
Change in antiretroviral regimen | 1% | 1% | 1% | 1%
Death | <1% | 1% | 1% | 1%
Discontinued due to adverse event | 4% | 9% | 5% | 12%
Discontinued for other reasons [Includes lost to follow-up, subject withdrawal, noncompliance, protocol violation and other reasons.] | 10% | 14% | 20% | 22%

Through Week 48, 84% and 73% of subjects in the emtricitabine + tenofovir DF group and the zidovudine/lamivudine group, respectively, achieved and maintained HIV-1 RNA <400 copies/mL (71% and 58% through Week 144). The difference in the proportion of subjects who achieved and maintained HIV-1 RNA <400 copies/mL through 48 weeks largely results from the higher number of discontinuations due to adverse events and other reasons in the zidovudine/lamivudine group in this open-label trial. In addition, 80% and 70% of subjects in the emtricitabine + tenofovir DF group and the zidovudine/lamivudine group, respectively, achieved and maintained HIV-1 RNA <50 copies/mL through Week 48 (64% and 56% through Week 144). The mean increase from baseline in CD4^+ cell count was 190 cells/mm^3 in the emtricitabine + tenofovir DF group and 158 cells/mm^3 in the zidovudine/lamivudine group at Week 48 (312 and 271 cells/mm^3 at Week 144).

Through 48 weeks, 7 subjects in the emtricitabine + tenofovir DF group and 5 subjects in the zidovudine/lamivudine group experienced a new CDC Class C event (10 and 6 subjects through 144 weeks).

14.2 iPrEx Trial

The iPrEx trial was a randomized double-blind placebo-controlled multinational study evaluating TRUVADA in 2,499 HIV-seronegative men or transgender women who have sex with men and with evidence of high risk behavior for HIV-1 infection. Evidence of high risk behavior included any one of the following reported to have occurred up to six months prior to study screening: no condom use during anal intercourse with an HIV-1 positive partner or a partner of unknown HIV status; anal intercourse with more than 3 sex partners; exchange of money, gifts, shelter or drugs for anal sex; sex with male partner and diagnosis of sexually transmitted infection; no consistent use of condoms with sex partner known to be HIV-1 positive.

All subjects received monthly HIV-1 testing, risk-reduction counseling, condoms and management of sexually transmitted infections. Of the 2,499 enrolled, 1,251 received TRUVADA and 1,248 received placebo. The mean age of subjects was 27 years, 5% were Asian, 9% Black, 18% White, and 72% Hispanic/Latino.

Subjects were followed for 4,237 person-years. The primary outcome measure for the study was the incidence of documented HIV seroconversion. At the end of treatment, emergent HIV-1 seroconversion was observed in 131 subjects, of which 48 occurred in the TRUVADA group and 83 occurred in the placebo group, indicating a 42% (95% CI: 18–60%) reduction in risk. Risk reduction was found to be higher (53%; 95% CI: 34–72%) among subjects who reported previous unprotected anal intercourse (URAI) at screening (732 and 753 subjects reported URAI within the last 12 weeks at screening in the TRUVADA and placebo groups, respectively). In a post-hoc case control study of plasma and intracellular drug levels in about 10% of study subjects, risk reduction appeared to be greatest in subjects with detectable intracellular tenofovir. Efficacy was therefore strongly correlated with adherence.

14.3 Partners PrEP Trial

The Partners PrEP trial was a randomized, double-blind, placebo-controlled 3-arm trial conducted in 4,758 serodiscordant heterosexual couples in Kenya and Uganda to evaluate the efficacy and safety of TDF (N=1,589) and FTC/TDF (N=1,583) versus (parallel comparison) placebo (N=1,586), in preventing HIV-1 acquisition by the uninfected partner.

All subjects received monthly HIV-1 testing, evaluation of adherence, assessment of sexual behavior, and safety evaluations. Women were also tested monthly for pregnancy. Women who became pregnant during the trial had study drug interrupted for the duration of the pregnancy and while breastfeeding. The uninfected partner subjects were predominantly male (61–64% across study drug groups), and had a mean age of 33–34 years.

Following 7,827 person-years of follow up, 82 emergent HIV-1 seroconversions were reported, with an overall observed seroincidence rate of 1.05 per 100 person-years. Of the 82 seroconversions, 13 and 52 occurred in partner subjects randomized to TRUVADA and placebo, respectively. Two of the 13 seroconversions in the TRUVADA arm and 3 of the 52 seroconversions in the placebo arm occurred in women during treatment interruptions for pregnancy. The risk reduction for TRUVADA relative to placebo was 75% (95% CI: 55–87%). In a post-hoc case control study of plasma drug levels in about 10% of study subjects, risk reduction appeared to be greatest in subjects with detectable plasma tenofovir. Efficacy was therefore strongly correlated with adherence.

16 HOW SUPPLIED/STORAGE AND HANDLING

TRUVADA tablets are available in bottles containing 30 tablets with child-resistant closure as follows:

- 200 mg of emtricitabine and 300 mg of tenofovir disoproxil fumarate (equivalent to 245 mg of tenofovir disoproxil) are blue, capsule-shaped, film-coated, debossed with "GILEAD" on one side and "701" on the other side
- Bottle of 3 NDC 68071-2112-3

STORAGE AND HANDLING

Store at 25 °C (77 °F), excursions permitted to 15 °C–30 °C (59 °F–86 °F) (see USP Controlled Room Temperature).

- Keep container tightly closed
- Dispense only in original container
- Do not use if seal over bottle opening is broken or missing

17 PATIENT COUNSELING INFORMATION

As a part of patient counseling, healthcare providers must review the TRUVADA Medication Guide with every uninfected individual taking TRUVADA to reduce the risk of acquiring HIV.

Advise the patient to read FDA-approved patient labeling (Medication Guide).

Important Information for All Patients and Uninfected Individuals

Advise patients and uninfected individuals that:

- The long term effects of TRUVADA are unknown.
- TRUVADA tablets are for oral ingestion only.
- Patients and uninfected individuals should not discontinue TRUVADA without first informing their physicians.
- Patients and uninfected individuals should remain under the care of a physician when using TRUVADA.
- It is important to take TRUVADA on a regular dosing schedule to avoid missing doses.
- Lactic acidosis and severe hepatomegaly with steatosis, including fatal cases, have been reported. Treatment with TRUVADA should be suspended in patients or uninfected individuals who develop clinical symptoms suggestive of lactic acidosis or pronounced hepatotoxicity (including nausea, vomiting, unusual or unexpected stomach discomfort, and weakness) [see Warnings and Precautions (5.1)] .
- Severe acute exacerbations of hepatitis B have been reported in patients who are coinfected with hepatitis B virus (HBV) and HIV-1 and have discontinued TRUVADA. Before initiating TRUVADA, test all patients and uninfected individuals for HBV. All patients who are infected with HBV need close medical follow-up for several months after stopping TRUVADA to monitor for exacerbations of hepatitis [see Warnings and Precautions (5.2)] .
- Renal impairment, including cases of acute renal failure and Fanconi syndrome, has been reported in association with the use of VIREAD. TRUVADA should be avoided with concurrent or recent use of a nephrotoxic agent (e.g., high-dose or multiple NSAIDs) [see Warnings and Precautions (5.3)] . Dosing interval of TRUVADA may need adjustment in HIV-1 infected patients with renal impairment. TRUVADA for a PrEP indication should not be used in HIV-1 uninfected individuals if estimated creatinine clearance is less than 60 mL/min. If a decrease in estimated creatinine clearance is observed in uninfected individuals while using TRUVADA for PrEP, evaluate potential causes and re-assess potential risks and benefits of continued use [see Dosage and Administration (2.4)] .
- Do not administer TRUVADA with ATRIPLA, COMPLERA, EMTRIVA, GENVOYA, ODEFSEY, STRIBILD, or VIREAD; or with drugs containing lamivudine, including Combivir (lamivudine/zidovudine), Dutrebis (lamivudine/raltegravir) , Epivir or Epivir-HBV (lamivudine), Epzicom (abacavir sulfate/lamivudine), Triumeq (abacavir sulfate/dolutegravir/lamivudine), or Trizivir (abacavir sulfate/lamivudine/zidovudine) [see Warnings and Precautions (5.4)] .
- Do not administer TRUVADA with HEPSERA [see Warnings and Precautions (5.4)] .
- Decreases in bone mineral density have been observed with the use of VIREAD or TRUVADA. Consider bone monitoring in patients and uninfected individuals who have a history of pathologic bone fracture or at risk for osteopenia [see Warnings and Precautions (5.5)].
- Patients and uninfected individuals should avoid doing things that can spread HIV-1 or HBV infection:
  - Do not share needles or other injection equipment.
  - Do not share personal items that can have blood or body fluids on them, like toothbrushes and razor blades.
  - Do not have any kind of sex without protection. Always practice safer sex by using a latex or polyurethane condom to lower the chance of sexual contact with semen, vaginal secretions, or blood.
  - Patients and uninfected individuals should not breastfeed because the drugs in TRUVADA can be passed to the baby in breast milk, and it is not known whether they can harm the baby. HIV-positive women should also not breastfeed because of the risk of passing the HIV-1 virus to the baby.

Treatment of HIV-1 Infection

When TRUVADA is used in the treatment of HIV-infection, advise patients that:

- TRUVADA is not a cure for HIV-1 infection and patients may continue to experience illnesses associated with HIV-1 infection, including opportunistic infections.
- It is important to take TRUVADA in a regular dosing schedule with combination therapy to avoid missing doses.
- All patients with HIV-1 should be tested for hepatitis B virus (HBV) before initiating and monitored after discontinuing taking TRUVADA.

Pre-Exposure Prophylaxis

When TRUVADA is used to reduce the risk of acquiring HIV-1, advise uninfected individuals about the importance of the following:

- Confirming that they are HIV-negative before starting to take TRUVADA to reduce the risk of acquiring HIV-1.
- TRUVADA should only be used as part of a complete prevention strategy including other prevention measures. In clinical trials, TRUVADA only protected some subjects from acquiring HIV-1.
- Using condoms consistently and correctly to lower the chance of sexual contact with any body fluids such as semen, vaginal secretions, or blood.
- Knowing their HIV status and the status of their partner(s).
- Getting tested regularly (at least every 3 months) for HIV-1 and ask their partner(s) to get tested as well.
- HIV-1 resistance substitutions may emerge in individuals with undetected HIV-1 infection who are taking TRUVADA, because TRUVADA alone does not constitute a complete regimen for HIV-1 treatment [see Warnings and Precautions (5.9)]
- Reporting any symptoms of acute HIV-1 infection (flu-like symptoms) to their healthcare provider immediately.
- Signs and symptoms of acute infection include: fever, headache, fatigue, arthralgia, vomiting, myalgia, diarrhea, pharyngitis, rash, night sweats, and adenopathy (cervical and inguinal).
- Getting tested for other sexually transmitted infections such as syphilis and gonorrhea that may facilitate HIV-1 transmission.
- Learning about sexual risk behavior and getting support to help reduce sexual risk behavior.
- Taking TRUVADA on a regular dosing schedule and strictly adhere to the recommended dosing schedule to reduce the risk of acquiring HIV-1. Uninfected individuals who miss doses are at greater risk of acquiring HIV-1 than those who do not miss doses [see Warnings and Precautions (5.9)].
- Women who are pregnant should learn about the risks and benefits of TRUVADA to reduce the risk of acquiring HIV-1 during their pregnancy.
- Encourage use of the Agreement Form for Initiating TRUVADA for PrEP of Sexually Acquired HIV-1 Infection.

COMPLERA, EMTRIVA, HARVONI, HEPSERA, GENVOYA, ODEFSEY, SOVALDI, STRIBILD, TRUVADA, and VIREAD are trademarks of Gilead Sciences, Inc., or its related companies. ATRIPLA is a trademark of Bristol-Myers Squibb & Gilead Sciences, LLC. All other trademarks referenced herein are the property of their respective owners.

Manufactured for and distributed by:

Gilead Sciences, Inc.
Foster City, CA 94404

21-752-GS-029

Medication Guide
TRUVADA® (tru-VAH-dah)
(emtricitabine and tenofovir disoproxil fumarate)
tablets

Read this Medication Guide before you start taking TRUVADA and each time you get a refill. There may be new information. This information does not take the place of talking to your healthcare provider about your medical condition or your treatment.

This Medication Guide provides information about two different ways that TRUVADA may be used (see the Medication Guide section " What is TRUVADA?" for important information about how TRUVADA may be used):

- to treat Human Immunodeficiency Virus-1 (HIV-1) infection, and
- to reduce the risk of getting HIV-1 infection in adults who are HIV-negative

HIV is the virus that causes AIDS (Acquired Immune Deficiency Syndrome).

What is the most important information I should know about TRUVADA?

TRUVADA can cause serious side effects, including:

- Too much lactic acid in your blood (lactic acidosis). Your body normally makes lactic acid, but too much lactic acid is a serious medical emergency. It can be treated, but it can also lead to death.

Call your healthcare provider right away if you get these symptoms:

- weakness or being more tired than usual
- unusual muscle pain
- being short of breath or fast breathing
- nausea, vomiting, and stomach-area pain
- cold or blue hands and feet
- feel dizzy or lightheaded
- fast or abnormal heartbeats

- Severe liver problems. Severe liver problems can happen in people who take TRUVADA. In some cases these liver problems can lead to death. Your liver may become large and tender. You may develop fat in your liver when you take TRUVADA.

Call your healthcare provider right away if you get the following symptoms:

- your skin or the white part of your eyes turns yellow
- dark "tea-colored" urine
- light-colored stools
- loss of appetite for several days or longer
- nausea
- stomach-area pain

You may be more likely to get lactic acidosis or severe liver problems if you are female, if you are very overweight (obese), or if you have been taking TRUVADA for a long time.

- If you also have hepatitis B virus (HBV) infection and take TRUVADA, your hepatitis B may become worse if you stop taking TRUVADA.
  - Do not stop taking TRUVADA without first talking to your healthcare provider.
  - Do not run out of TRUVADA. Refill your prescription or talk to your healthcare provider before your TRUVADA is all gone.
  - If your healthcare provider stops TRUVADA, your healthcare provider will need to watch you closely for several months to check your hepatitis B infection, or give you a medication to treat hepatitis B.

Tell your healthcare provider about any new or unusual symptoms you may have after you stop taking TRUVADA.

For more information about side effects, see the section " What are the possible side effects of TRUVADA?" in this Medication Guide.

Other important information for people who take TRUVADA to help reduce their risk of getting HIV-1 infection:

Before taking TRUVADA to reduce your risk of getting HIV-1 infection:

- You must be HIV-negative to start TRUVADA. You must get tested to make sure that you do not already have HIV-1 infection.
- Do not take TRUVADA to reduce the risk of getting HIV-1 unless you are confirmed to be HIV-negative.
- Many HIV-1 tests can miss HIV-1 infection in a person who has recently become infected. If you have flu-like symptoms, you could have recently become infected with HIV-1. Tell your healthcare provider if you had a flu-like illness within the last month before starting TRUVADA or at any time while taking TRUVADA. Symptoms of new HIV-1 infection include:

- tiredness
- fever
- joint or muscle aches
- headache

- sore throat
- vomiting or diarrhea
- rash
- night sweats
- enlarged lymph nodes in the neck or groin

While you are taking TRUVADA to reduce your risk of getting HIV-1:

- Just taking TRUVADA may not keep you from getting HIV-1.
- You must continue using safer sex practices while you are taking TRUVADA to reduce your risk of getting HIV-1.
- You must stay HIV-negative to keep taking TRUVADA to reduce your risk of infection.
  - Know your HIV-1 status and the HIV-1 status of your partners.
  - Get tested for HIV-1 at least every 3 months or when your healthcare provider tells you.
  - Get tested for other sexually transmitted infections such as syphilis and gonorrhea. These infections make it easier for HIV-1 to infect you.
  - If you think you were exposed to HIV-1, tell your healthcare provider right away. They may want to do more tests to be sure you are still HIV-negative.
  - Get information and support to help reduce risky sexual behavior.
  - Have fewer sex partners.
  - Do not miss any doses of TRUVADA. Missing doses may increase your risk of getting HIV-1 infection.
- If you do become HIV-positive, you need more medicine than TRUVADA alone to treat HIV-1. TRUVADA by itself is not a complete treatment for HIV-1.
  - If you have HIV-1 and take only TRUVADA, over time your HIV-1 may become harder to treat.

See the section " What should I avoid while taking TRUVADA?" and talk to your healthcare provider for more information about how to prevent HIV-1 infection.

What is TRUVADA?

TRUVADA contains the prescription medicines emtricitabine (EMTRIVA®) and tenofovir disoproxil fumarate (VIREAD®). TRUVADA is used:

- to treat HIV-1 infection when used with other HIV-1 medicines in adults and children who weigh at least 37 pounds (at least 17 kg).
- to help reduce the risk of getting HIV-1 infection when used with safer sex practices in:
  - HIV-negative men who have sex with men, who are at high risk of getting infected with HIV-1 through sex.
  - Male-female sex partners when one partner has HIV-1 infection and the other does not.

Use of TRUVADA to treat HIV-1 infection:

- When used with other HIV-1 medicines to treat HIV-1 infection, TRUVADA may help:
  - Reduce the amount of HIV-1 in your blood. This is called "viral load".
  - Increase the number of CD4+ (T) cells in your blood that help fight off other infections.

Reducing the amount of HIV-1 and increasing the CD4+ (T) cells in your blood may help improve your immune system. This may reduce your risk of death or getting infections that can happen when your immune system is weak (opportunistic infections).

- TRUVADA does not cure HIV-1 or AIDS. If you have HIV-1 infection, you must keep taking HIV-1 medicines to control HIV-1 infection and decrease HIV-related illnesses.
- It is not known if TRUVADA is safe and effective in children with HIV-1 infection who weigh less than 37 pounds (less than 17 kg).

Use of TRUVADA to reduce the risk of HIV-1 infection:

- When used with safer sex practices, TRUVADA may help to reduce the risk of getting HIV-1 infection:
  - TRUVADA works better to reduce the risk of getting HIV-1 when the medicines are in your bloodstream before you are exposed to HIV-1.

Who should not take TRUVADA?

For people using TRUVADA to reduce the risk of getting HIV-1 infection:

TRUVADA can only help reduce your risk of getting HIV-1 before you are infected. Do not take TRUVADA to help reduce your risk of getting HIV-1 if:

- you already have HIV-1 infection. If you are HIV-positive, you need to take other medicines with TRUVADA to treat HIV-1. TRUVADA by itself is not a complete treatment for HIV-1.
- you do not know your HIV-1 infection status. You may already be HIV-positive. You need to take other HIV-1 medicines with TRUVADA to treat HIV-1.

What should I tell my healthcare provider before taking TRUVADA?

Tell your healthcare provider if you:

- have liver problems including hepatitis B virus infection
- have kidney problems or receive kidney dialysis treatment
- have bone problems
- have any other medical conditions
- are pregnant or plan to become pregnant. It is not known if TRUVADA can harm your unborn baby.
  If you are a female who is taking TRUVADA to reduce the risk of getting HIV-1 infection and you become pregnant while taking TRUVADA, talk to your healthcare provider to decide if you should keep taking TRUVADA.
  Pregnancy Registry: A pregnancy registry collects information about your health and the health of your baby. There is a pregnancy registry for women who take medicines to treat or prevent HIV-1 during pregnancy. For more information about the registry and how it works, talk to your healthcare provider.
- are breastfeeding or plan to breastfeed.
  - You should not breastfeed if you have HIV-1 because of the risk of passing HIV-1 to your baby.
  - Do not breastfeed if you take TRUVADA. TRUVADA can pass to your baby in your breast milk.
  - Talk with your healthcare provider about the best way to feed your baby.

Tell your healthcare provider about all the medicines you take, including prescription and over-the-counter medicines, vitamins, and herbal supplements.

Do not take TRUVADA if you also take any of the medicines listed below:

- medicines which also contain emtricitabine or tenofovir disoproxil fumarate, (ATRIPLA®, COMPLERA®, EMTRIVA, GENVOYA®, ODEFSEY®, STRIBILD®, or VIREAD). These medicines contain one or more of the same active ingredients as TRUVADA.
- medicines which contain tenofovir alafenamide (GENVOYA® or ODEFSEY®)
- medicines which contain lamivudine (Combivir, Dutrebis, Epivir, Epivir-HBV, Epzicom, Triumeq, or Trizivir)
- adefovir (HEPSERA®)

TRUVADA may interact with other medicines. Especially tell your healthcare provider if you take:

- didanosine (Videx EC)
- atazanavir (Reyataz)
- ledipasvir with sofosbuvir (HARVONI®)

- darunavir (Prezista)
- lopinavir with ritonavir (Kaletra)

Your healthcare provider may need to check you more often or change your dose if you take any of these medicines and TRUVADA.

Know the medicines you take. Keep a list of them to show your healthcare provider or pharmacist when you get a new medicine.

How should I take TRUVADA?

- Take TRUVADA exactly as prescribed.
- Take TRUVADA by mouth, with or without food.
- Children who take TRUVADA are prescribed a lower strength tablet than adults.
  - Children should swallow the tablet whole. Tell your healthcare provider if your child cannot swallow the tablet whole, because they may need a different HIV-1 medicine.
  - Your healthcare provider will change the dose of TRUVADA as needed based on your child's weight.
- TRUVADA is usually taken 1 time each day. Take TRUVADA at the same time each day to keep TRUVADA blood levels constant.
  - If you have kidney problems, your healthcare provider may tell you to take TRUVADA less often.
- Do not miss any doses of TRUVADA. Missing a dose lowers the amount of medicine in your blood.
- If you miss a dose of TRUVADA, take it as soon as you remember that day. Do not take more than 1 dose of TRUVADA in a day. Do not take 2 doses at the same time to make up for a missed dose. Call your healthcare provider or pharmacist if you are not sure what to do.
- Do not change your dose or stop taking TRUVADA without first talking with your healthcare provider. Stay under a healthcare provider's care when taking TRUVADA.
- Refill your TRUVADA prescription before you run out of medicine.
- If you take too much TRUVADA, call your healthcare provider or go to the nearest hospital emergency room right away.
- If you take TRUVADA to treat HIV-1 infection, you need to take other HIV-1 medicines. Your healthcare provider will tell you what medicines to take and how to take them.
- If you take TRUVADA to reduce your risk of getting HIV-1:
  - you must also use other methods to reduce your risk of getting HIV-1. See the section " What should I avoid while taking TRUVADA?" in this Medication Guide.
  - Take TRUVADA every day, not just when you think you have been exposed to HIV-1.

What should I avoid while taking TRUVADA?

While taking TRUVADA, avoid doing things that increase your risk of getting HIV-1 or spreading HIV-1 to other people.

- See the section " What is the most important information I should know about TRUVADA?" at the beginning of this Medication Guide.
- Do not have any kind of sex without protection. Always practice safer sex by using a latex or polyurethane condom, to lower the chance of sexual contact with semen, vaginal fluids, or blood.
- Do not share personal items that can have blood or body fluids on them, such as toothbrushes and razor blades.
- Do not share or re-use needles or other injection equipment.

Ask your healthcare provider if you have any questions about how to prevent getting HIV-1 or spreading HIV-1 to other people.

What are the possible side effects of TRUVADA?

TRUVADA may cause serious side effects, including:

- See " What is the most important information I should know about TRUVADA?"
- New or worse kidney problems, including kidney failure. If you had kidney problems in the past or take another medicine that can cause kidney problems, your healthcare provider may do blood tests to check your kidneys before you start and while you are taking TRUVADA. Your healthcare provider may tell you to take TRUVADA less often, or to stop taking TRUVADA if you have kidney problems.
- Bone problems can happen in some people who take TRUVADA. Bone problems include bone pain, or softening or thinning of bones, which may lead to fractures. Your healthcare provider may need to do tests to check your bones.
- Changes in body fat can happen in people who take HIV-1 medicines. The exact cause and long-term health effects of these problems are not known. The changes may include:
  - increased amount of fat in the upper back and neck ("buffalo hump"), breast, and around the middle of your body (trunk)
  - loss of fat from the legs, arms, and face
- Changes in your immune system (Immune Reconstitution Syndrome) can happen when an HIV-1-infected person starts taking HIV-1 medicines. Your immune system may get stronger, and can then cause you to develop inflammation in areas of your body where infections may have been hiding for a long time. This inflammation may cause you to have minor symptoms, such as fever, but inflammation can also lead to serious problems. Tell your healthcare provider right away if you start having any new symptoms after starting TRUVADA for treatment of HIV-1 infection.

The most common side effects of TRUVADA in people taking TRUVADA to treat HIV-1 infection include:

- diarrhea
- nausea
- tiredness
- headache

- dizziness
- depression
- problems sleeping
- abnormal dreams
- rash

Common side effects in people who take TRUVADA to reduce the risk of getting HIV-1 infection include:

- stomach-area (abdomen) pain

- headache

- decreased weight

Tell your healthcare provider if you have any side effect that bothers you or that does not go away.

These are not all the possible side effects of TRUVADA. For more information, ask your healthcare provider or pharmacist.

Call your doctor for medical advice about side effects. You may report side effects to FDA at 1-800-FDA-1088.

How should I store TRUVADA?

- Store TRUVADA at room temperature between 68 °F to 77 °F (20 °C to 25 °C).
- Keep TRUVADA in its original container and keep the container tightly closed.
- Do not use TRUVADA if seal over bottle opening is broken or missing.

Keep TRUVADA and all other medicines out of reach of children.

General information about TRUVADA.

Medicines are sometimes prescribed for purposes other than those listed in a Medication Guide. Do not use TRUVADA for a condition for which it was not prescribed. Do not give TRUVADA to other people, even if they have the same symptoms you have. It may harm them.

This Medication Guide summarizes the most important information about TRUVADA. If you would like more information, talk with your healthcare provider. You can ask your healthcare provider or pharmacist for information about TRUVADA that is written for health professionals. For more information, call 1-800-445-3235 or go to www.TRUVADA.com.

What are the ingredients in TRUVADA?

Active ingredients: emtricitabine and tenofovir disoproxil fumarate.

Inactive ingredients: Croscarmellose sodium, lactose monohydrate, magnesium stearate, microcrystalline cellulose, and pregelatinized starch (gluten free). The 200 mg/300 mg strength tablets are coated with Opadry II Blue Y-30-10701, which contains FD&C Blue #2 aluminum lake, hypromellose 2910, lactose monohydrate, titanium dioxide, and triacetin. The 167 mg/250 mg, 133 mg/200 mg, and 100 mg/150 mg strength tablets are coated with Opadry II Blue, which contains FD&C Blue #2 aluminum lake, hypromellose 2910, lactose monohydrate, titanium dioxide, and triacetin.

Manufactured for and distributed by:
Gilead Sciences, Inc.
Foster City, CA 94404
21-752-GS-030

This Medication Guide has been approved by the U.S. Food and Drug Administration.

Revised: April 2016

PRINCIPAL DISPLAY PANEL -

<